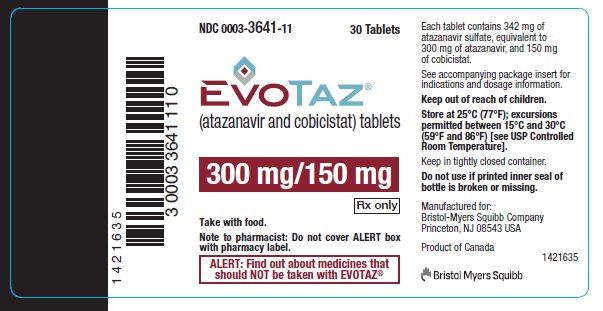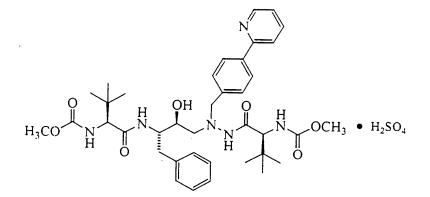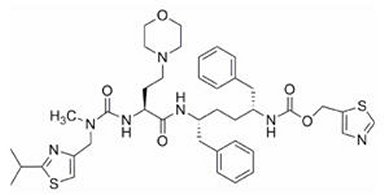 DRUG LABEL: EVOTAZ
NDC: 0003-3641 | Form: TABLET
Manufacturer: E.R. Squibb & Sons, L.L.C.
Category: prescription | Type: HUMAN PRESCRIPTION DRUG LABEL
Date: 20250512

ACTIVE INGREDIENTS: ATAZANAVIR SULFATE 300 mg/1 1; COBICISTAT 150 mg/1 1
INACTIVE INGREDIENTS: MICROCRYSTALLINE CELLULOSE; CROSCARMELLOSE SODIUM; SODIUM STARCH GLYCOLATE TYPE A POTATO; STEARIC ACID; MAGNESIUM STEARATE; HYDROXYPROPYL CELLULOSE (1600000 WAMW); SILICON DIOXIDE; CROSPOVIDONE (120 .MU.M)

HIGHLIGHTS OF PRESCRIBING INFORMATION

These highlights do not include all the information needed to use EVOTAZ safely and effectively. See full prescribing information for EVOTAZ.
EVOTAZ® (atazanavir and cobicistat) tablet, for oral use
Initial U.S. Approval: 2015

RECENT MAJOR CHANGES

Contraindications (4) | 05/2025

1 INDICATIONS AND USAGE

EVOTAZ is a two-drug combination of atazanavir, a human immunodeficiency virus (HIV-1) protease inhibitor, and cobicistat, a CYP3A inhibitor indicated for use in combination with other antiretroviral agents for the treatment of HIV‑1 infection in adults and pediatric patients weighing at least 35 kg. (1)

Limitations of Use

Use of EVOTAZ in treatment-experienced patients should be guided by the number of baseline primary protease inhibitor resistance substitutions. (1)

2 DOSAGE AND ADMINISTRATION

- Pretreatment testing: Renal laboratory testing should be performed in all patients prior to initiation of EVOTAZ and continued during treatment with EVOTAZ. Hepatic testing should be performed in patients with underlying liver disease prior to initiation of EVOTAZ and continued during treatment with EVOTAZ. (2.1)
- Recommended dosage: One tablet once daily, taken orally with food in adults and pediatric patients weighing at least 35 kg. (2.2)
- Renal impairment: EVOTAZ is not recommended for use in treatment-experienced patients with end-stage renal disease managed with hemodialysis. (2.3, 8.6)
- Hepatic impairment: EVOTAZ is not recommended in patients with any degree of hepatic impairment. (2.4, 8.7)

3 DOSAGE FORMS AND STRENGTHS

- Tablets: 300 mg of atazanavir and 150 mg of cobicistat. (3)

4 CONTRAINDICATIONS

- EVOTAZ is contraindicated in patients with previously demonstrated hypersensitivity (e.g., Stevens-Johnson syndrome, erythema multiforme, or toxic skin eruptions) to any of the components of this product. (4)
- EVOTAZ is contraindicated with drugs that are strong inducers of CYP3A4 due to the potential for loss of therapeutic effect and development of possible resistance. (4)
- EVOTAZ is contraindicated with certain drugs for which altered plasma concentrations are associated with serious and/or life-threatening events or loss of therapeutic effect. (4)

5 WARNINGS AND PRECAUTIONS

- Cardiac conduction abnormalities: PR interval prolongation may occur in some patients. Consider ECG monitoring in patients with preexisting conduction system disease or when administered with other drugs that may prolong the PR interval. (5.1, 6, 7.3, 12.2, 17)
- Severe skin reactions: Discontinue if severe rash develops. (5.2, 6.1, 17)
- Assess creatinine clearance (CLcr) before initiating treatment. Consider alternative medications that do not require dosage adjustments in patients with renal impairment. (5.3)
- When cobicistat, a component of EVOTAZ, is used in combination with a tenofovir disoproxil fumarate (tenofovir DF)-containing regimen, cases of acute renal failure and Fanconi syndrome have been reported. (5.4)
- When used with tenofovir DF, assess urine glucose and urine protein at baseline and monitor CLcr, urine glucose, and urine protein. Monitor serum phosphorus in patients with or at risk for renal impairment. Coadministration with tenofovir DF is not recommended in patients with CLcr below 70 mL/min or in patients also receiving a nephrotoxic agent. (5.4)
- Chronic kidney disease has been reported during postmarketing surveillance in patients with HIV-1 treated with atazanavir, with or without ritonavir. Consider alternatives in patients at high risk for renal disease or with preexisting renal disease. Monitor renal laboratory tests prior to therapy and during treatment with EVOTAZ. Consider discontinuation of EVOTAZ in patients with progressive renal disease. (5.5)
- Nephrolithiasis and cholelithiasis have been reported. Consider temporary interruption or discontinuation. (5.6, 6)
- Hepatotoxicity: Patients with hepatitis B or C are at risk of increased transaminases or hepatic decompensation. Monitor hepatic laboratory tests prior to therapy and during treatment. (2.5, 5.7, 8.7)
- Antiretrovirals that are not recommended: EVOTAZ is not recommended for use with ritonavir or products containing ritonavir, or in combination with other antiretroviral drugs that require CYP3A inhibition to achieve adequate exposures (e.g., other protease inhibitors and elvitegravir). (5.9)
- Hyperbilirubinemia: Most patients experience asymptomatic increases in indirect bilirubin, which is reversible upon discontinuation. If a concomitant transaminase increase occurs, evaluate for alternative etiologies. (5.10, 6)
- Patients receiving EVOTAZ may develop immune reconstitution syndrome (5.11), new onset or exacerbations of diabetes mellitus/hyperglycemia (5.12, 6), and redistribution/accumulation of body fat (5.13).
- Hemophilia: Spontaneous bleeding may occur and additional factor VIII may be required. (5.14)

6 ADVERSE REACTIONS

Most common adverse reactions seen with atazanavir coadministered with cobicistat (greater than 5%, Grades 2-4) are jaundice and rash. (6.1)

To report SUSPECTED ADVERSE REACTIONS, contact Bristol-Myers Squibb at 1-800-721-5072 or FDA at 1-800-FDA-1088 or www.fda.gov/medwatch.

7 DRUG INTERACTIONS

Coadministration of EVOTAZ can alter the concentration of other drugs and other drugs may alter the concentration of EVOTAZ, which may result in known or potentially significant drug interactions. The potential drug-drug interactions must be considered prior to and during therapy. (4, 7, 12.3)

8 USE IN SPECIFIC POPULATIONS

- Pregnancy: EVOTAZ is not recommended during pregnancy and should not be initiated in pregnant individuals; use of an alternative regimen is recommended. (2.5, 8.1)
- Pediatrics: EVOTAZ is not recommended for patients weighing less than 35 kg. (8.4)

FULL PRESCRIBING INFORMATION

1 INDICATIONS AND USAGE

1.1 Indications

EVOTAZ® is indicated in combination with other antiretroviral agents for the treatment of human immunodeficiency virus (HIV-1) infection in the following populations [see Dosage and Administration (2.2, 2.3)]:

- Adult patients
- Pediatric patients weighing at least 35 kg.

1.2 Limitations of Use

Use of EVOTAZ in treatment-experienced patients should be guided by the number of baseline primary protease inhibitor resistance substitutions [see Clinical Pharmacology (12.4)].

2 DOSAGE AND ADMINISTRATION

2.1 Laboratory Testing Prior to Initiation and During Treatment with EVOTAZ

Renal Testing

Renal laboratory testing should be performed in all patients prior to initiation of EVOTAZ and continued during treatment with EVOTAZ. Renal laboratory testing should include estimated creatinine clearance, serum creatinine, and urinalysis with microscopic examination [see Warnings and Precautions (5.5,5.6)]. Cobicistat decreases estimated creatinine clearance due to inhibition of tubular secretion of creatinine without affecting actual renal glomerular function [see Warnings and Precautions (5.3)].

When coadministering EVOTAZ with tenofovir disoproxil fumarate (tenofovir DF), assess estimated creatinine clearance, urine glucose, and urine protein at baseline and routinely monitor during treatment. In patients with chronic kidney disease, also monitor serum phosphorus [see Warnings and Precautions (5.4)].

Hepatic Testing

Hepatic laboratory testing should be performed in patients with underlying liver disease prior to initiation of EVOTAZ and continued during treatment with EVOTAZ [see Warnings and Precautions (5.7)].

2.2 Recommended Dosage

EVOTAZ is a fixed-dose tablet containing 300 mg of atazanavir and 150 mg of cobicistat. The recommended dosage of EVOTAZ is one tablet taken once daily orally with food [see Clinical Pharmacology (12.3)] in both treatment-naive and treatment-experienced patients with HIV-1:

- Adult patients
- Pediatric patients weighing at least 35 kg

Administer EVOTAZ in conjunction with other antiretroviral agents [see Drug Interactions (7)]. Dose separation may be required when taken with H2-receptor antagonists or proton-pump inhibitors [see Drug Interactions (7.2, 7.3)].

2.3 Dosage in Patients with Renal Impairment

EVOTAZ is not recommended in treatment-experienced patients with HIV-1 who have end-stage renal disease managed with hemodialysis [see Use in Specific Populations (8.6) and Clinical Pharmacology (12.3)].

EVOTAZ coadministered with tenofovir DF is not recommended in patients with estimated creatinine clearance below 70 mL/min. Coadministration of EVOTAZ and tenofovir DF in combination with concomitant or recent use of a nephrotoxic agent is not recommended [see Warnings and Precautions (5.4) and Adverse Reactions (6.1)].

2.4 Not Recommended in Patients with Any Degree of Hepatic Impairment

EVOTAZ is not recommended in patients with any degree of hepatic impairment [see Warnings and Precautions (5.7), Use in Specific Populations (8.7), and Clinical Pharmacology (12.3)].

2.5 Not Recommended During Pregnancy

EVOTAZ is not recommended for use during pregnancy and should not be initiated in pregnant individuals due to substantially lower exposures of cobicistat and consequently, lower exposures of atazanavir, during the second and third trimesters. An alternative regimen is recommended for individuals who become pregnant during therapy with EVOTAZ [see Use in Specific Populations (8.1)].

3 DOSAGE FORMS AND STRENGTHS

EVOTAZ tablets contain 342 mg atazanavir sulfate, equivalent to 300 mg of atazanavir, and 150 mg of cobicistat and are oval, biconvex, pink, film-coated, and debossed with “3641” on one side and plain on the other side.

4 CONTRAINDICATIONS

The concomitant use of EVOTAZ and the following drugs in Table 1, are contraindicated due to the potential for serious and/or life-threatening events or loss of therapeutic effect [see Warnings and Precautions (5.8, 5.9), Drug Interactions (7), and Clinical Pharmacology (12.3)].

EVOTAZ is contraindicated:

- in patients with previously demonstrated clinically significant hypersensitivity (e.g., Stevens-Johnson syndrome, erythema multiforme, or toxic skin eruptions) to any of the components of this product [see Warnings and Precautions (5.2)].
- when coadministered with drugs that strongly induce CYP3A4, which may lead to lower exposure of EVOTAZ resulting in potential loss of efficacy and development of possible resistance (Table 5).
- when coadministered with drugs that are highly dependent on CYP3A or UGT1A1 for clearance, and for which elevated plasma concentrations of the interacting drugs are associated with serious and/or life-threatening events (see Table 5).

For additional information, including clinical comments and potential impact on exposure levels associated with drugs that are contraindicated with EVOTAZ, refer to Table 5 [see Drug Interactions (7.3)].

Coadministration is contraindicated with, but not limited to, the following drugs:

Table 1: Drugs Contraindicated with EVOTAZ
Drug Class | Drugs within class that are contraindicated with EVOTAZ
Alpha 1-adrenoreceptor antagonist | alfuzosin
Antianginal | ranolazine
Antiarrhythmics | dronedarone
Anticonvulsants | carbamazepine, phenobarbital, phenytoin
Antigout | colchicine (when used in patients with hepatic and/or renal impairment)
Antimycobacterials | rifampin
Antineoplastics | apalutamide, encorafenib, irinotecan, ivosidenib
Antipsychotics | lurasidone, pimozide
Ergot Derivatives | dihydroergotamine, ergotamine, methylergonovine
Hepatitis C Direct-Acting Antivirals | elbasvir/grazoprevir; glecaprevir/pibrentasvir
Herbal Products | St. John’s wort (Hypericum perforatum)
Hormonal Contraceptives | drospirenone/ethinyl estradiol
Lipid-modifying Agents | lomitapide, lovastatin, simvastatin
Non-nucleoside Reverse Transcriptase Inhibitor | nevirapine
Phosphodiesterase-5 (PDE-5) Inhibitor | sildenafila when administered for the treatment of pulmonary arterial hypertension
Protease Inhibitors | indinavir
Sedative/hypnotics | triazolam, orally administered midazolamb
a Refer to Table 5 for sildenafil when administered for erectile dysfunction [see Drug Interactions (7.3)].
b Refer to Table 5 for parenterally administered midazolam [see Drug Interactions (7.3)].

5 WARNINGS AND PRECAUTIONS

5.1 Cardiac Conduction Abnormalities

Atazanavir prolongs the PR interval of the electrocardiogram in some patients. In healthy participants and in participants with HIV-1 treated with atazanavir, abnormalities in atrioventricular (AV) conduction were asymptomatic and generally limited to first-degree AV block. There have been reports of second-degree AV block and other conduction abnormalities [see Adverse Reactions (6.1) and Overdosage (10)]. In clinical trials of atazanavir in participants with HIV-1 that included electrocardiograms, asymptomatic first-degree AV block was observed in 6% of participants treated with atazanavir (n=920) and 5% of participants (n=118) treated with atazanavir coadministered with ritonavir. Because of limited clinical experience in patients with preexisting conduction system disease (e.g., marked first-degree AV block or second- or third-degree AV block), consider ECG monitoring in these patients [see Clinical Pharmacology (12.2)].

5.2 Severe Skin Reactions

Cases of Stevens-Johnson syndrome, erythema multiforme, and toxic skin eruptions, including drug rash, eosinophilia and systemic symptoms (DRESS) syndrome, have been reported in patients receiving atazanavir [see Contraindications (4) and Adverse Reactions (6.1)]. EVOTAZ should be discontinued if severe rash develops.

Mild-to-moderate maculopapular skin eruptions have also been reported in atazanavir clinical trials. These reactions had a median time to onset of 7.3 weeks and median duration of 1.4 week and generally did not result in treatment discontinuation.

5.3 Effects on Serum Creatinine

Cobicistat decreases estimated creatinine clearance due to inhibition of tubular secretion of creatinine without affecting actual renal glomerular function. This effect should be considered when interpreting changes in estimated creatinine clearance in patients initiating EVOTAZ, particularly in patients with medical conditions or receiving drugs needing monitoring with estimated creatinine clearance.

Prior to initiating therapy with EVOTAZ, assess estimated creatinine clearance [see Dosage and Administration (2.1)]. Dosage recommendations are not available for drugs that require dosage adjustments in cobicistat-treated patients with renal impairment [see Adverse Reactions (6.1), Drug Interactions (7.3), and Clinical Pharmacology (12.2)]. Consider alternative medications that do not require dosage adjustments in patients with renal impairment.

Although cobicistat may cause modest increases in serum creatinine and modest declines in estimated creatinine clearance without affecting renal glomerular function, patients who experience a confirmed increase in serum creatinine of greater than 0.4 mg/dL from baseline should be closely monitored for renal safety.

5.4 New Onset or Worsening Renal Impairment When Used with Tenofovir DF

Renal impairment, including cases of acute renal failure and Fanconi syndrome, has been reported when cobicistat was used in an antiretroviral regimen that contained tenofovir DF. Therefore, coadministration of EVOTAZ and tenofovir DF is not recommended in patients who have an estimated creatinine clearance below 70 mL/min [see Dosage and Administration (2.3)].

• When EVOTAZ is used with tenofovir DF, document urine glucose and urine protein at baseline and perform routine monitoring of estimated creatinine clearance, urine glucose, and urine protein during treatment.

• Measure serum phosphorus in patients with or at risk for renal impairment.

• Coadministration of EVOTAZ and tenofovir DF in combination with concomitant or recent use of a nephrotoxic agent is not recommended.

In a clinical trial over 144 weeks (N=692), 10 (2.9%) participants treated with atazanavir coadministered with cobicistat and tenofovir DF and 11 (3.2%) participants treated with atazanavir coadministered with ritonavir and tenofovir DF discontinued study drug due to a renal adverse event. Seven of the 10 participants (2.0% overall) in the cobicistat group had laboratory findings consistent with proximal renal tubulopathy leading to study drug discontinuation, compared to 7 of 11 participants (2.0% overall) in the ritonavir group. One participant in the cobicistat group had renal impairment at baseline (e.g., estimated creatinine clearance less than 70 mL/min). The laboratory findings in these 7 participants treated with cobicistat, with evidence of proximal tubulopathy improved but did not completely resolve in all participants upon discontinuation of cobicistat coadministered with atazanavir and tenofovir DF. Renal replacement therapy was not required in any participant.

5.5 Chronic Kidney Disease

Chronic kidney disease in patients with HIV-1 treated with atazanavir, with or without ritonavir, has been reported during postmarketing surveillance. Reports included biopsy-proven cases of granulomatous interstitial nephritis associated with the deposition of atazanavir drug crystals in the renal parenchyma. Consider alternatives to EVOTAZ in patients at high risk for renal disease or with preexisting renal disease. Renal laboratory testing (including serum creatinine, estimated creatinine clearance, and urinalysis with microscopic examination) should be conducted in all patients prior to initiating therapy with EVOTAZ and continued during treatment with EVOTAZ. Expert consultation is advised for patients who have confirmed renal laboratory abnormalities while taking EVOTAZ. In patients with progressive kidney disease, discontinuation of EVOTAZ may be considered [see Dosage and Administration (2.1, 2.3) and Adverse Reactions (6.1)].

5.6 Nephrolithiasis and Cholelithiasis

Cases of nephrolithiasis and/or cholelithiasis have been reported during postmarketing surveillance in patients with HIV-1 receiving atazanavir therapy. Some patients required hospitalization for additional management and some had complications. Because these events were reported voluntarily during clinical practice, estimates of frequency cannot be made. If signs or symptoms of nephrolithiasis and/or cholelithiasis occur, temporary interruption or discontinuation of therapy may be considered [see Adverse Reactions (6, 6.1)].

5.7 Hepatotoxicity

Patients with underlying hepatitis B or C virus or marked elevations in transaminases may be at increased risk for developing further transaminase elevations or hepatic decompensation. In these patients, hepatic laboratory testing should be conducted prior to initiating therapy with EVOTAZ and during treatment [see Dosage and Administration (2.4) and Use in Specific Populations (8.7)].

5.8 Risk of Serious Adverse Reactions or Loss of Virologic Response Due to Drug Interactions

Initiation of EVOTAZ, a CYP3A inhibitor, in patients receiving medications metabolized by CYP3A or initiation of medications metabolized by CYP3A in patients already receiving EVOTAZ, may increase plasma concentrations of medications metabolized by CYP3A.

Initiation of medications that inhibit or induce CYP3A may increase or decrease concentrations of EVOTAZ, respectively.

Increased concentrations of EVOTAZ may lead to:

• clinically significant adverse reactions, potentially leading to severe, life threatening, or fatal events from higher exposures of concomitant medications.

• clinically significant adverse reactions from higher exposures of EVOTAZ.

Decreased concentrations of EVOTAZ may lead to:

• loss of therapeutic effect of EVOTAZ and possible development of resistance.

See Table 5 for steps to prevent or manage these possible and known significant drug interactions, including dosing recommendations [see Drug Interactions (7.3)]. Consider the potential for drug interactions prior to and during EVOTAZ therapy; review concomitant medications during EVOTAZ therapy; and monitor for the adverse reactions associated with the concomitant medications [see Contraindications (4) and Drug Interactions (7)].

When used with concomitant medications, EVOTAZ may result in different drug interactions than those observed or expected with atazanavir coadministered with ritonavir. Complex or unknown mechanisms of drug interactions preclude extrapolation of drug interactions with atazanavir coadministered with ritonavir to certain EVOTAZ interactions [see Drug Interactions (7) and Clinical Pharmacology (12.3)].

5.9 Antiretrovirals that are Not Recommended

EVOTAZ is not recommended in combination with other antiretroviral drugs that require CYP3A inhibition to achieve adequate exposures (e.g., other HIV protease inhibitors or elvitegravir) because dosing recommendations for such combinations have not been established and coadministration may result in decreased plasma concentrations of the antiretroviral agents, leading to loss of therapeutic effect and development of resistance.

EVOTAZ is not recommended in combination with ritonavir or products containing ritonavir due to similar effects of cobicistat and ritonavir on CYP3A.

See Drug Interactions (7) for additional recommendations on use with other antiretroviral agents.

5.10 Hyperbilirubinemia

Most patients taking atazanavir experience asymptomatic elevations in indirect (unconjugated) bilirubin related to inhibition of UDP-glucuronosyltransferase (UGT). This hyperbilirubinemia is reversible upon discontinuation of atazanavir. Hepatic transaminase elevations that occur with hyperbilirubinemia should be evaluated for alternative etiologies. No long-term safety data are available for patients experiencing persistent elevations in total bilirubin greater than 5 times the upper limit of normal (ULN). Alternative antiretroviral therapy to EVOTAZ may be considered if jaundice or scleral icterus associated with bilirubin elevations presents cosmetic concerns for patients [see Adverse Reactions (6)].

5.11 Immune Reconstitution Syndrome

Immune reconstitution syndrome has been reported in patients treated with combination antiretroviral therapy, including atazanavir, a component of EVOTAZ. During the initial phase of combination antiretroviral treatment, patients whose immune system responds may develop an inflammatory response to indolent or residual opportunistic infections (such as Mycobacterium avium, cytomegalovirus, Pneumocystis jirovecii pneumonia, or tuberculosis), which may necessitate further evaluation and treatment.

Autoimmune disorders (such as Graves’ disease, polymyositis, Guillain-Barré syndrome, and autoimmune hepatitis) have also been reported to occur in the setting of immune reconstitution; however, the time to onset is more variable, and can occur many months after initiation of treatment.

5.12 Diabetes Mellitus/Hyperglycemia

New-onset diabetes mellitus, exacerbation of preexisting diabetes mellitus, and hyperglycemia have been reported during postmarketing surveillance in patients with HIV-1 receiving protease inhibitor therapy. Some patients required either initiation or dose adjustments of insulin or oral hypoglycemic agents for treatment of these events. In some cases, diabetic ketoacidosis has occurred. In those patients who discontinued protease inhibitor therapy, hyperglycemia persisted in some cases. Because these events have been reported voluntarily during clinical practice, estimates of frequency cannot be made and a causal relationship between protease inhibitor therapy and these events has not been established.

5.13 Fat Redistribution

Redistribution/accumulation of body fat including central obesity, dorsocervical fat enlargement (buffalo hump), peripheral wasting, facial wasting, breast enlargement, and “cushingoid appearance” have been observed in patients receiving antiretroviral therapy. The mechanism and long-term consequences of these events are currently unknown. A causal relationship has not been established.

5.14 Hemophilia

There have been reports of increased bleeding, including spontaneous skin hematomas and hemarthrosis, in patients with hemophilia type A and B treated with protease inhibitors. In some patients, additional factor VIII was given. In more than half of the reported cases, treatment with protease inhibitors was continued or reintroduced. A causal relationship between protease inhibitor therapy and these events has not been established.

6 ADVERSE REACTIONS

The following adverse reactions are discussed in greater detail in other sections of the labeling:

- cardiac conduction abnormalities [see Warnings and Precautions (5.1)]
- rash [see Warnings and Precautions (5.2)]
- effects on serum creatinine [see Warnings and Precautions (5.3)]
- new onset or worsening renal impairment when used with tenofovir DF [see Warnings and Precautions (5.4)]
- chronic kidney disease [see Warnings and Precautions (5.5)]
- nephrolithiasis and cholelithiasis [see Warnings and Precautions (5.6)]
- hepatotoxicity [see Warnings and Precautions (5.7)]
- hyperbilirubinemia [see Warnings and Precautions (5.10)]

For additional safety information about atazanavir and cobicistat, consult the full prescribing information for these individual products.

6.1 Clinical Trial Experience

Because clinical trials are conducted under widely varying conditions, adverse reaction rates observed in the clinical trials of a drug cannot be directly compared to rates in the clinical trials of another drug and may not reflect the rates observed in practice.

Adverse Reactions from Clinical Trial Experience in Adult Participants

The safety of atazanavir and cobicistat coadministered as single agents is based on Week 144 data from a Phase 3 trial, Study GS-US-216-0114, in which 692 antiretroviral treatment-naive participants with HIV-1 received:

- atazanavir coadministered with cobicistat and emtricitabine/tenofovir DF (N=344) or
- atazanavir coadministered with ritonavir and emtricitabine/tenofovir DF (N=348).

The most common adverse reactions (Grades 2-4) and reported in ≥5% of participants in the atazanavir coadministered with cobicistat group were jaundice (6%) and rash (5%).

The proportion of participants who discontinued study treatment due to adverse events regardless of severity, was 11% in both the atazanavir coadministered with cobicistat and atazanavir coadministered with ritonavir groups. Table 2 lists the frequency of adverse reactions (Grades 2-4) occurring in at least 2% of participants in the atazanavir coadministered with cobicistat group in Study GS-US-216-0114.

Table 2: Selected Adverse Reactionsa (Grades 2-4) Reported in ≥2% of Treatment-Naive Adults with HIV-1 in the Atazanavir Coadministered with Cobicistat Group in Study GS-US-216-0114 (Week 144 analysis)
 | Atazanavir coadministered with cobicistat and emtricitabine/tenofovir DF (n=344) | Atazanavir coadministered with ritonavir and emtricitabine/tenofovir DF (n=348)
Jaundice | 6% | 3%
Rashb | 5% | 4%
Ocular icterus | 4% | 2%
Nausea | 2% | 2%
Diarrhea | 2% | 1%
Headache | 2% | 1%

a Frequencies of adverse reactions are based on Grades 2-4 adverse events attributed to study drugs.
b Rash events include dermatitis allergic, drug hypersensitivity, pruritus generalized, eosinophilic pustular folliculitis, rash, rash generalized, rash macular, rash maculopapular, rash morbilliform, rash papular, and urticaria.

Less Common Adverse Reactions

Selected adverse reactions of at least moderate severity (≥ Grade 2) occurring in less than 2% of participants receiving atazanavir coadministered with cobicistat and emtricitabine/tenofovir DF are listed below. These events have been included because of investigator’s assessment of potential causal relationship and were considered serious or have been reported in more than one participant treated with atazanavir coadministered with cobicistat and reported with greater frequency compared with the atazanavir coadministered with ritonavir group.

Gastrointestinal Disorders: vomiting, upper abdominal pain

General Disorders and Administration Site Conditions: fatigue

Musculoskeletal and Connective Tissue Disorders: rhabdomyolysis

Psychiatric Disorders: depression, abnormal dreams, insomnia

Renal and Urinary Disorders: nephropathy, Fanconi syndrome acquired, nephrolithiasis

Laboratory Abnormalities

The frequency of laboratory abnormalities (Grades 3-4) occurring in at least 2% of participants in the atazanavir coadministered with cobicistat group in Study GS-US-216-0114 is presented in Table 3.

Table 3: Laboratory Abnormalities (Grades 3-4) Reported in ≥2% of Treatment-Naive Adults with HIV-1 in the Atazanavir Coadministered with Cobicistat Group in Study GS-US-216-0114 (Week 144 analysis)
 | 144 weeks Atazanavir coadministered with cobicistat and emtricitabine/tenofovir DF | 144 weeks Atazanavir coadministered with ritonavir and emtricitabine/tenofovir DF
Laboratory Parameter Abnormality | (n=344) | (n=348)
Total Bilirubin (>2.5 × ULN) | 73% | 66%
Creatine Kinase (≥10.0 × ULN) | 8% | 9%
Urine RBC (Hematuria) (>75 RBC/HPF) | 6% | 3%
ALT (>5.0 × ULN) | 6% | 3%
AST (>5.0 × ULN) | 4% | 3%
GGT (>5.0 × ULN) | 4% | 2%
Serum Amylasea (>2.0 × ULN) | 4% | 2%
Urine Glucose (Glycosuria ≥1000 mg/dL) | 3% | 3%
Neutrophils (<750/mm^3) | 3% | 2%
Serum Glucose (Hyperglycemia) (≥250 mg/dL) | 2% | 2%
a For participants with serum amylase >1.5 × upper limit of normal, lipase test was also performed. The frequency of increased lipase (Grades 3-4) occurring in the atazanavir coadministered with cobicistat group (N=46) and atazanavir coadministered with ritonavir group (N=35) was 7% and 3%, respectively.

Increase in Serum Creatinine: Cobicistat, a component of EVOTAZ, has been shown to increase serum creatinine and decrease estimated creatinine clearance due to inhibition of tubular secretion of creatinine without affecting actual renal glomerular function [see Warnings and Precautions (5.3) and Clinical Pharmacology (12.2)]. In Study GS-US-216-0114, increases in serum creatinine and decreases in estimated creatinine clearance occurred early in treatment in the atazanavir coadministered with cobicistat group, after which they stabilized. The mean (± SD) change in estimated glomerular filtration rate (eGFR) by Cockcroft-Gault method after 144 weeks of treatment was −15.1 ± 16.5 mL/min in the atazanavir coadministered with cobicistat group and −8.0 ± 16.8 mL/min in the atazanavir coadministered with ritonavir group.

Serum Lipids

Changes from baseline in total cholesterol, HDL-cholesterol, LDL-cholesterol, and triglycerides are presented in Table 4. In both groups, mean values for serum lipids remained within the normal range for each laboratory test. The clinical significance of these changes is unknown.

Table 4: Lipid Values, Mean Change from Baseline, Reported in Treatment-Naive Adults with HIV-1 Receiving Atazanavir Coadministered with Cobicistat and Emtricitabine/Tenofovir DF or Atazanavir Coadministered with Ritonavir and Emtricitabine/Tenofovir DF in Study GS-US-216-0114 (Week 144 analysis)
 | Atazanavir coadministered with cobicistat and emtricitabine/tenofovir DF |  | Atazanavir coadministered with ritonavir and emtricitabine/tenofovir DF
 | Baseline mg/dL | Week 144 change from baselinea | Baseline mg/dL | Week 144 change from baselinea
Total Cholesterol (fasted) | 163 [N=219] | +11 [N=219] | 165 [N=227] | +13 [N=227]
HDL-cholesterol (fasted) | 43 [N=218] | +7 [N=218] | 43 [N=228] | +6 [N=228]
LDL-cholesterol (fasted) | 102 [N=218] | +11 [N=218] | 104 [N=228] | +16 [N=228]
Triglycerides (fasted) | 130 [N=219] | +14 [N=219] | 131 [N=227] | +14 [N=227]
a The change from baseline is the mean of within-participant changes from baseline for participants with both baseline and Week 144 values and excludes participants receiving an HMG-CoA reductase inhibitor drug.

Adverse Reactions from Clinical Trial Experience in Pediatric Participants

Although no clinical trial with EVOTAZ as the fixed-dose tablet was conducted in a pediatric population, the safety of atazanavir coadministered with cobicistat plus two nucleoside reverse transcriptase inhibitors was evaluated in treatment-experienced virologically suppressed participants with HIV-1 between the ages of 12 to less than 18 years (N=14) through Week 48 in an open-label clinical trial (Study GS-US-216-0128) [see Clinical Studies (14.2)]. Results from this study showed that the safety profile of atazanavir and cobicistat coadministered with a background regimen was similar to that in adults.

6.2 Postmarketing Experience

See the full prescribing information for atazanavir for postmarketing information on atazanavir.

7 DRUG INTERACTIONS

7.1 Potential for EVOTAZ to Affect Other Drugs

Atazanavir is an inhibitor of CYP3A and UGT1A1 and a weak inhibitor of CYP2C8. Cobicistat is an inhibitor of CYP3A and CYP2D6. The transporters that cobicistat inhibits include P-glycoprotein (P-gp), BCRP, OATP1B1 and OATP1B3.

Coadministration of EVOTAZ with drugs highly dependent on CYP3A for clearance and for which elevated plasma concentrations are associated with serious and/or life-threatening events is contraindicated [see Contraindications (4)]. Coadministration of EVOTAZ and drugs primarily metabolized by CYP3A, UGT1A1 and/or CYP2D6 or drugs that are substrates of P-gp, BCRP, OATP1B1 and/or OATP1B3 may result in increased plasma concentrations of the other drug that could increase or prolong its therapeutic effects and adverse reactions which may require dose adjustments and/or additional monitoring as shown in Table 5. Use of EVOTAZ is not recommended when coadministered with drugs highly dependent on CYP2C8 for clearance with narrow therapeutic indices (e.g., paclitaxel, repaglinide) [see Clinical Pharmacology (12.3; Table 7)].

7.2 Potential for Other Drugs to Affect EVOTAZ

Atazanavir and cobicistat are CYP3A4 substrates; therefore, drugs that induce CYP3A4 may decrease atazanavir and cobicistat plasma concentrations and reduce the therapeutic effect of EVOTAZ, leading to development of resistance to atazanavir (see Table 5). Cobicistat is also metabolized by CYP2D6 to a minor extent.

Coadministration of EVOTAZ with other drugs that inhibit CYP3A4 may increase the plasma concentrations of cobicistat and atazanavir (see Table 5).

Atazanavir solubility decreases as pH increases. Reduced plasma concentrations of atazanavir are expected if proton-pump inhibitors, antacids, buffered medications, or H2-receptor antagonists are administered with EVOTAZ (see Table 5) [see Dosage and Administration (2.2)].

7.3 Established and Other Potentially Significant Drug Interactions

Table 5 provides dosing recommendations as a result of drug interactions with the components of EVOTAZ. These recommendations are based either on observed drug interactions in studies of cobicistat, atazanavir, or atazanavir coadministered with ritonavir or predicted drug interactions based on the expected magnitude of interaction and potential for serious events or loss of therapeutic effect of EVOTAZ [see Contraindications (4), Warnings and Precautions (5.8), and Clinical Pharmacology (12.3)].

Table 5: Established and Other Potentially Significant Drug Interactions with EVOTAZ: Alteration in Dose or Regimen May Be Recommended Based on Drug Interaction Studiesa or Predicted Interactions
Concomitant Drug Class: Specific Drugs | Effectb on Concentration | Clinical Comment
HIV Antiretroviral Agents: Nucleoside and Nucleotide Reverse Transcriptase Inhibitors (NRTIs and NtRTIs)
didanosine buffered formulations enteric-coated (EC) capsules | ↓ atazanavir ↓ didanosine | It is recommended that EVOTAZ be given with food 2 hours before or 1 hour after didanosine buffered formulations. Simultaneous administration of didanosine EC and atazanavir with food results in a decrease in didanosine exposure. Thus, EVOTAZ and didanosine EC should be administered at different times.
tenofovir disoproxil fumarate | ↓ atazanavir ↑ tenofovir | Patients receiving EVOTAZ and tenofovir should be monitored for tenofovir-associated adverse reactions [see Warnings and Precautions (5.4)].
HIV Antiretroviral Agents: Non-nucleoside Reverse Transcriptase Inhibitors (NNRTIs)
nevirapine | ↓ atazanavir ↑ nevirapine | Coadministration of EVOTAZ with nevirapine is contraindicated due to potential for loss of atazanavir therapeutic effect and development of resistance, and potential for nevirapine-associated adverse reactions [see Contraindications (4)].
efavirenz | ↓ atazanavir ↓ cobicistat ↔ efavirenz | Coadministration of EVOTAZ with efavirenz is not recommended because it may result in a loss of therapeutic effect and development of resistance to atazanavir.
etravirine | ↓ atazanavir ↓ cobicistat | Coadministration of EVOTAZ with etravirine is not recommended because it may result in the loss of therapeutic effect and development of resistance to atazanavir.
HIV Antiretroviral Agents: CCR5 Antagonist
maraviroc | ↑ maraviroc | When coadministering maraviroc and EVOTAZ, patients should receive maraviroc 150 mg twice daily.
HIV Antiretroviral Agents: Protease Inhibitor
indinavir |  | Coadministration with indinavir is contraindicated [see Contraindications (4)].; Both atazanavir and indinavir are associated with indirect (unconjugated) hyperbilirubinemia.
ritonavir or products containing ritonavir | ↑ atazanavir | Coadministration of EVOTAZ and ritonavir or ritonavir-containing regimens is not recommended due to similar effects of cobicistat and ritonavir on CYP3A [see Warnings and Precautions (5.9)].
Hepatitis C Antiviral Agents
sofosbuvir/velpatasvir/ voxilaprevir | ↑ voxilaprevir | Coadministration with EVOTAZ is not recommended.
Other Agents
Alpha 1-adrenoreceptor antagonist: alfuzosin | ↑ alfuzosin | Coadministration of EVOTAZ with alfuzosin is contraindicated due to the potential for increased alfuzosin concentrations, which can result in hypotension [see Contraindications (4)].
Antacids and buffered medications (please also see H2-receptor antagonists and proton-pump inhibitors below) | ↓ atazanavir | With concomitant use, administer a minimum of 2 hours apart.
Antianginal: ranolazine | ↑ ranolazine | Coadministration of EVOTAZ with ranolazine is contraindicated due to the potential for serious and/or life-threatening reactions [see Contraindications (4)].
Antiarrhythmics: dronedarone | ↑ dronedarone | Coadministration of EVOTAZ with dronedarone is contraindicated due to potential for serious and/or life-threatening reactions such as cardiac arrhythmias [see Contraindications (4)].
amiodarone, quinidine; lidocaine (systemic),; disopyramide, flecainide; mexiletine, propafenone digoxin | ↑ other antiarrhythmics; ↑ digoxin | Clinical monitoring is recommended upon coadministration with antiarrhythmics.; When coadministering EVOTAZ with digoxin, titrate the digoxin dose and monitor digoxin concentrations.
Antibacterials (macrolide or ketolide antibiotics): clarithromycin erythromycin telithromycin | ↑ atazanavir ↑ cobicistat ↑ clarithromycin ↑ erythromycin ↑ telithromycin | Consider alternative antibiotics.
Anticancer Agents: irinotecan | ↑ irinotecan | Coadministration of EVOTAZ with irinotecan is contraindicated due to potential for increased irinotecan toxicity [see Contraindications (4)].
(e.g., dasatinib, nilotinib, vinblastine, vincristine) | ↑ other anticancer agents | A decrease in the dosage or an adjustment of the dosing interval of dasatinib or nilotinib may be necessary upon coadministration with EVOTAZ. Consult the dasatinib and nilotinib full prescribing information for dosing instructions.; For vincristine and vinblastine, monitor for hematologic or gastrointestinal side effects.
Anticoagulants: Direct-acting oral anticoagulants (DOACs) apixaban | ↑ apixaban | Due to potentially increased bleeding risk, dosing recommendations for coadministration of apixaban with EVOTAZ depends on the apixaban dose. Refer to apixaban dosing instructions for coadministration with strong CYP3A4 and P-gp inhibitors in apixaban prescribing information.
rivaroxaban | ↑ rivaroxaban | Coadministration of EVOTAZ and rivaroxaban is not recommended because it may lead to increased bleeding risk.
betrixaban dabigatran etexilate edoxaban | ↑ betrixaban ↑ dabigatran ↑ edoxaban | Due to potentially increased bleeding risk, dosing recommendations for coadministration of betrixaban, dabigatran, or edoxaban with a P-gp inhibitor such as EVOTAZ depends on DOAC indication and renal function. Refer to DOAC dosing instructions for coadministration with P-gp inhibitors in DOAC prescribing information.
warfarin | warfarin: effect unknown | Monitor the International Normalized Ratio (INR) when EVOTAZ is coadministered with warfarin.
Anticonvulsants: carbamazepine, phenobarbital, phenytoin; Anticonvulsants with CYP3A induction effects that are NOT contraindicated (e.g., eslicarbazepine, oxcarbazepine) | ↓ atazanavir; ↓ cobicistat; ↓ atazanavir; ↓ cobicistat | Coadministration of EVOTAZ with carbamazepine, phenobarbital, or phenytoin is contraindicated due to potential for loss of therapeutic effect and development of resistance [see Contraindications (4)].; Consider alternative anticonvulsant or antiretroviral therapy to avoid potential changes in exposures. If coadministration is necessary, monitor for lack or loss of virologic response.
Anticonvulsants that are metabolized by CYP3A (e.g., clonazepam) | ↑ clonazepam | Clinical monitoring of anticonvulsants is recommended with EVOTAZ coadministration.
Other anticonvulsants (e.g., lamotrigine) | lamotrigine: effects unknown | Monitoring of lamotrigine concentrations is recommended with EVOTAZ coadministration.
Antidepressants: Selective Serotonin Reuptake Inhibitors (SSRIs) (e.g., paroxetine) | SSRIs: effects unknown | When coadministering with SSRIs, TCAs, or trazodone, careful dose titration of the antidepressant to the desired effect, using the lowest feasible initial or maintenance dose, and monitoring for antidepressant response are recommended.
Tricyclic Antidepressants (TCAs) (e.g., amitriptyline, desipramine, imipramine, nortriptyline) | ↑ TCAs
Other Antidepressants (e.g., trazodone) | ↑ trazodone
Antifungals: ketoconazole, itraconazole | ↑ atazanavir ↑ cobicistat ↑ ketoconazole ↑ itraconazole | Specific dosing recommendations are not available for coadministration of EVOTAZ with either itraconazole or ketoconazole.
voriconazole | effects unknown | Coadministration with voriconazole is not recommended unless the benefit/risk assessment justifies the use of voriconazole.
Antigout: colchicine | ↑ colchicine | Coadministration of EVOTAZ with colchicine in patients with renal or hepatic impairment is contraindicated due to the potential for serious and/or life-threatening reactions [see Contraindications (4)].; Recommended dosage of colchicine when administered with EVOTAZ:; Treatment of gout flares: 0.6 mg (1 tablet) for 1 dose, followed by 0.3 mg (half tablet) 1 hour later. Treatment course should be repeated no earlier than 3 days.; Prophylaxis of gout flares: If the original regimen was 0.6 mg twice a day, the regimen should be adjusted to 0.3 mg once a day.; If the original regimen was 0.6 mg once a day, the regimen should be adjusted to 0.3 mg once every other day.; Treatment of familial Mediterranean fever (FMF): Maximum daily dose of 0.6 mg (may be given as 0.3 mg twice a day).
Antimycobacterials: Rifabutin | atazanavir: effect unknown; cobicistat: effect unknown; ↑ rifabutin | A rifabutin dose reduction of up to 75% (e.g., 150 mg every other day or 3 times per week) is recommended. Increased monitoring for rifabutin-associated adverse reactions, including neutropenia and uveitis, is warranted.
rifampin | ↓ atazanavir; ↓ cobicistat | Coadministration with rifampin is contraindicated due to potential for loss of therapeutic effect and development of resistance [see Contraindications (4)].
Antineoplastics:; apalutamide | ↓ atazanavir; ↓cobicistat | Coadministration with apalutamide is contraindicated due to the potential for substantial decrease in plasma concentrations of atazanavir and cobicistat, which may result in loss of virologic response of EVOTAZ and possible resistance to atazanavir or to other protease inhibitors. [see Contraindications (4)].; Mechanism: The mechanism of interaction is CYP3A4 induction by apalutamide.
ivosidenib | ↓ atazanavir; ↓ cobicistat; ↑ ivosidenib | Coadministration with ivosidenib is contraindicated due to the potential for loss of virologic response of EVOTAZ, development of resistance, and risk of serious adverse events such as QT interval prolongation. [see Contraindications (4)].; Mechanism: The mechanism of interaction is CYP3A4 induction by ivosidenib.
encorafenib | ↓ atazanavir; ↓ cobicistat; ↑ encorafenib | Coadministration with encorafenib is contraindicated due to the potential for loss of virologic response of EVOTAZ, development of resistance, and risk of serious adverse events such as QT interval prolongation. [see Contraindications (4)].; Mechanism: The mechanism of interaction is CYP3A4 induction by encorafenib.
Antiplatelets: ticagrelor | ↑ ticagrelor | Coadministration with ticagrelor is not recommended due to the potential increase of the antiplatelet activity of ticagrelor.
clopidogrel | ↓ clopidogrel active metabolite | Coadministration with clopidogrel is not recommended due to the potential reduction of the antiplatelet activity of clopidogrel.
prasugrel | ↔ prasugrel active metabolite | No dose adjustment is needed when prasugrel is coadministered with atazanavir and/or cobicistat.
Antipsychotics: lurasidone | ↑ lurasidone | Coadministration with lurasidone is contraindicated due to the potential for serious and/or life-threatening reactions [see Contraindications (4)].
pimozide | ↑ pimozide | Coadministration with pimozide is contraindicated due to the potential for serious and/or life-threatening reactions such as cardiac arrhythmias [see Contraindications (4)].
quetiapine | ↑ quetiapine | Initiation of EVOTAZ in patients taking quetiapine: Consider alternative antiretroviral therapy to avoid increases in quetiapine exposures. If coadministration is necessary, reduce the quetiapine dose to 1/6 of the current dose and monitor for quetiapine-associated adverse reactions. Refer to the quetiapine prescribing information for recommendations on adverse reaction monitoring.; Initiation of quetiapine in patients taking EVOTAZ: Refer to the quetiapine prescribing information for initial dosing and titration of quetiapine.
(e.g., perphenazine, risperidone, thioridazine) | ↑ antipsychotic | A decrease in the dose of antipsychotics that are metabolized by CYP3A or CYP2D6 may be needed when coadministered with EVOTAZ.
Beta-agonist (inhaled): salmeterol | ↑ salmeterol | Coadministration with salmeterol is not recommended due to an increased risk of cardiovascular adverse reactions associated with salmeterol, including QT prolongation, palpitations, and sinus tachycardia.
Beta-Blockers: (e.g., metoprolol, carvedilol, timolol) | ↔ atazanavir ↑ beta-blockers | Clinical monitoring is recommended when beta-blockers that are metabolized by CYP2D6 are coadministered with EVOTAZ.
Calcium channel blockers: (e.g., amlodipine, diltiazem, felodipine, nifedipine, and verapamil) | ↑ calcium channel blocker | Clinical monitoring is recommended for coadministration with calcium channel blockers metabolized by CYP3A. ECG monitoring is recommended.
Corticosteroids: e.g., betamethasone budesonide ciclesonide dexamethasone fluticasone methylprednisolone mometasone triamcinolone | ↓ atazanavir; ↓ cobicistat; ↑ corticosteroids | Coadministration with oral dexamethasone or other systemic corticosteroids that induce CYP3A may result in loss of therapeutic effect and development of resistance to atazanavir. Consider alternative corticosteroids.; Coadministration with corticosteroids (all routes of administration) whose exposures are significantly increased by strong CYP3A inhibitors can increase the risk for Cushing’s syndrome and adrenal suppression.; Alternative corticosteroids including beclomethasone, prednisone, and prednisolone (whose PK and/or PD are less affected by strong CYP3A inhibitors relative to other studied steroids) should be considered, particularly for long-term use.
Kinase inhibitors:; fostamatinib | ↑ R406 active metabolite of fostamatinib | Coadministration with fostamatinib may increase the plasma concentration of R406, the active metabolite of fostamatinib. Monitor for toxicities of R406 exposure resulting in dose-related adverse events such as hepatotoxicity and neutropenia. Fostamatinib dose reduction may be required.
Endothelin receptor antagonists: bosentan | ↓ atazanavir ↓ cobicistat ↑ bosentan | Initiation of bosentan in patients taking EVOTAZ:; For patients who have been receiving EVOTAZ for at least 10 days, start bosentan at 62.5 mg once daily or every other day based on individual tolerability.; Initiation of EVOTAZ in patients taking bosentan:; Discontinue bosentan at least 36 hours before starting EVOTAZ. After at least 10 days following initiation of EVOTAZ, resume bosentan at 62.5 mg once daily or every other day based on individual tolerability.; Switching from atazanavir coadministered with ritonavir to EVOTAZ:; Maintain bosentan dose.
Gonadotropin releasing hormone antagonist Receptor (GnRH):; elagolix | ↓ atazanavir; ↓ cobicistat; ↑ elagolix | Coadministration of EVOTAZ with elagolix may result in decreased plasma concentrations of atazanavir and/or cobicistat. Concomitant use of elagolix 200 mg twice daily with EVOTAZ for more than 1 month is not recommended due to the potential risk of adverse events such as bone loss and hepatic transaminase elevations. Limit concomitant use of elagolix 150 mg once daily with EVOTAZ to 6 months. In addition, monitor virologic responses due to the potential reduction in atazanavir/cobicistat exposure.
Ergot Derivatives:; dihydroergotamine, ergotamine, methylergonovine | ↑ ergot derivatives | Coadministration of EVOTAZ with ergot derivatives is contraindicated due to the potential for serious and/or life-threatening events such as acute ergot toxicity, characterized by peripheral vasospasm and ischemia of the extremities and other tissues [see Contraindications (4)].
Hepatitis C Direct-Acting Antivirals: elbasvir/grazoprevir | ↑ grazoprevir | Coadministration of EVOTAZ with elbasvir/grazoprevir is contraindicated due to increased risk of ALT elevations [see Contraindications (4)].
glecaprevir/pibrentasvir | ↑ glecaprevir ↑ pibrentasvir | Coadministration of EVOTAZ with glecaprevir/ pibrentasvir is contraindicated due to increased risk of ALT elevations [see Contraindications (4)].
Herbal Products: St. John’s wort (Hypericum perforatum) | ↓ atazanavir ↓ cobicistat | Coadministration of products containing St. John’s wort and EVOTAZ is contraindicated due to potential for loss of therapeutic effect and development of resistance [see Contraindications (4)].
H2‑Receptor antagonists (H2 RA): (e.g., famotidine) | ↓ atazanavir | Coadministration of EVOTAZ with tenofovir DF and an H2RA in treatment-experienced patients is not recommended.; Administer EVOTAZ either at the same time or at a minimum of 10 hours after a dose of the H2RA. The dose of the H2RA should not exceed a dose comparable to famotidine 40 mg twice daily in treatment-naive patients or 20 mg twice daily in treatment-experienced patients.
Lipid-modifying agents: Other lipid-modifying agents: lomitapide | ↑ lomitapide | Coadministration with lomitapide is contraindicated due to the potential for risk of markedly increased transaminase levels and hepatoxicity [see Contraindications (4)].
HMG-CoA reductase inhibitors: lovastatin simvastatin | ↑lovastatin ↑simvastatin | Coadministration with lovastatin or simvastatin is contraindicated due to the potential for serious reactions such as myopathy, including rhabdomyolysis [see Contraindications (4)].
Other HMG-CoA reductase inhibitors: atorvastatin, fluvastatin, pravastatin, rosuvastatin | ↑ HMG-CoA reductase inhibitors | Coadministration of EVOTAZ with atorvastatin is not recommended.; For HMG-CoA reductase inhibitors that are not contraindicated with EVOTAZ, start with the lowest recommended dose and titrate while monitoring for safety (e.g., myopathy). Dosage recommendations with rosuvastatin are as follows.; Rosuvastatin dose should not exceed 10 mg/day.
Hormonal contraceptives: drospirenone/ethinyl estradiol | ↑ drospirenone | Coadministration with drospirenone-containing products is contraindicated due to the potential for drospirenone-associated hyperkalemia [see Contraindications (4)].
(e.g., progestin/estrogen) | progestin and estrogen: effects unknown | No data are available to make recommendations on the coadministration of EVOTAZ and oral or other hormonal contraceptives. Alternative nonhormonal forms of contraception should be considered.
Immunosuppressants: (e.g., cyclosporine, everolimus, sirolimus, tacrolimus) | ↑ immunosuppressants | Therapeutic concentration monitoring is recommended for these immunosuppressants when coadministered with EVOTAZ.
Narcotic analgesics: For treatment of opioid dependence: buprenorphine, naloxone, methadone | buprenorphine or buprenorphine/naloxone: effects unknown; methadone: effects unknown | Initiation of buprenorphine, buprenorphine/naloxone or methadone in patients taking EVOTAZ: Carefully titrate the dose of buprenorphine, buprenorphine/naloxone or methadone to the desired effect; use the lowest feasible initial or maintenance dose.; Initiation of EVOTAZ in patients taking buprenorphine, buprenorphine/naloxone or methadone: A dose adjustment for buprenorphine, buprenorphine/naloxone or methadone may be needed. Monitor clinical signs and symptoms.
fentanyl | ↑ fentanyl | When EVOTAZ is coadministered with fentanyl, careful monitoring of therapeutic and adverse effects of fentanyl (including potentially fatal respiratory depression) is recommended.
tramadol | ↑ tramadol | When EVOTAZ is coadministered with tramadol, a decreased dose of tramadol may be needed.
Phosphodiesterase-5 (PDE-5) inhibitors: avanafil, sildenafil, tadalafil, vardenafil | ↑ PDE-5 inhibitors | Use of PDE-5 inhibitors for pulmonary arterial hypertension (PAH): Coadministration of EVOTAZ with sildenafil is contraindicated due to the potential for sildenafil-associated adverse events (which include visual disturbances, hypotension, priapism, and syncope) [see Contraindications (4)].; Tadalafil: The following dose adjustments are recommended for the use of tadalafil with EVOTAZ: Initiation of tadalafil in patients taking EVOTAZ:
 |  |  | - For patients receiving EVOTAZ for at least one week, start tadalafil at 20 mg once daily. Increase to 40 mg once daily based on individual tolerability.
 |  | Initiation of EVOTAZ in patients taking tadalafil:
 |  |  | - Avoid the use of tadalafil when starting EVOTAZ. Stop tadalafil at least 24 hours before starting EVOTAZ. At least one week after starting EVOTAZ, resume tadalafil at 20 mg once daily. Increase to 40 mg once daily based on individual tolerability.
 |  | Patients switching from atazanavir coadministered with ritonavir to EVOTAZ:
 |  |  | - Maintain tadalafil dose.
 |  | Use of PDE-5 inhibitors for erectile dysfunction:; Avanafil: Not recommended because a safe and effective dose of avanafil has not been established. Sildenafil: Reduced dosage to 25 mg every 48 hours with increased monitoring for adverse reactions. Tadalafil: Reduced dosage to 10 mg every 72 hours with increased monitoring for adverse reactions. Vardenafil: Reduced dosage to no more than 2.5 mg every 72 hours with increased monitoring for adverse reactions.
Proton-pump inhibitors (PPI): (e.g., omeprazole) | ↓ atazanavir | In treatment-naive patients, administer EVOTAZ a minimum of 12 hours after administration of the PPI. The dose of the PPI should not exceed a dose comparable to omeprazole 20 mg daily.; In treatment-experienced patients, coadministration of EVOTAZ with PPI is not recommended.
Sedatives/Hypnotics: Benzodiazepines midazolam (oral) triazolam | ↑ midazolam ↑ triazolam | Coadministration of triazolam or orally administered midazolam is contraindicated due to the potential for serious and/or life-threatening events such as prolonged or increased sedation or respiratory depression. Triazolam and orally administered midazolam are extensively metabolized by CYP3A4 [see Contraindications (4)].
Other Benzodiazepines: clorazepate diazepam estazolam flurazepam parenterally administered midazolam | ↑ sedatives/hypnotics | Parenterally administered midazolam: Coadministration should be done in a setting which ensures close clinical monitoring and appropriate medical management in case of respiratory depression and/or prolonged sedation. Dosage reduction for midazolam should be considered, especially if more than a single dose of midazolam is administered.
Other Sedatives/Hypnotics: buspirone, zolpidem |  | With other sedatives/hypnotics that are CYP3A metabolized, a dose reduction may be necessary and clinical monitoring is recommended.
a For magnitude of interactions see Clinical Pharmacology (12.3; Table 7).
b ↑ = Increase, ↓ = Decrease, ↔ = No change.

7.4 Drugs with No Observed or Predicted Interactions with the Components of EVOTAZ

Based on known metabolic profiles, clinically significant drug interactions are not expected between EVOTAZ and acetaminophen, atenolol, dapsone, fluconazole, trimethoprim/sulfamethoxazole, or azithromycin [see Clinical Pharmacology (12.3; Table 7)].

8 USE IN SPECIFIC POPULATIONS

8.1 Pregnancy

Pregnancy Exposure Registry

There is a pregnancy exposure registry that monitors pregnancy outcomes in individuals exposed to EVOTAZ during pregnancy. Healthcare providers are encouraged to register patients by calling the Antiretroviral Pregnancy Registry (APR) at 1-800-258-4263.

Risk Summary

EVOTAZ is not recommended for use during pregnancy and should not be initiated in pregnant individuals [see Dosage and Administration (2.5)]; use of an alternative regimen is recommended for individuals who become pregnant during therapy with EVOTAZ. Pharmacokinetic data from studies conducted in pregnant individuals receiving cobicistat showed substantially lower exposures during the second and third trimesters, and consequently also for the coadministered antiretroviral agent. Consult the full prescribing information for cobicistat for additional information. Pharmacokinetic data from the evaluation of atazanavir and cobicistat in a limited number of pregnant individuals showed a similar trend in lower exposures of the antiretroviral component, atazanavir.

Prospective pregnancy data from the APR are not sufficient to adequately assess the risk of birth defects or miscarriage. Atazanavir use during pregnancy has been evaluated in a limited number of individuals. Available data from the APR show no increase in the risk of overall major birth defects for atazanavir compared with the background rate for major birth defects of 2.7% in a U.S. reference population of the Metropolitan Atlanta Congenital Defects Program (MACDP) (see Data). The rate of miscarriage is not reported in the APR. The estimated background rate of miscarriage in clinically recognized pregnancies in the U.S. general population is 15−20%.

In animal reproduction studies, no evidence of adverse developmental outcomes was observed following oral administration of the components of EVOTAZ (atazanavir or cobicistat) to pregnant rats and rabbits (see Data). During organogenesis in the rat and rabbit, atazanavir exposures (AUC) were similar to those observed at the human clinical dose (300 mg/day atazanavir boosted with 100 mg/day ritonavir), while exposures were up to 1.4 (rats) and 3.3 (rabbits) times human exposures at the maximal recommended human dose (MRHD) of 150 mg (see Data).

Clinical Considerations

EVOTAZ is not recommended for use during pregnancy and should not be initiated in pregnant individuals. An alternative regimen is recommended for individuals who become pregnant during therapy with EVOTAZ (see Risk Summary).

Maternal Adverse Reactions

Atazanavir

Reports of lactic acidosis syndrome, sometimes fatal, and symptomatic hyperlactatemia have occurred in pregnant individuals using atazanavir in combination with nucleoside analogues, which are associated with an increased risk of lactic acidosis syndrome.

Hyperbilirubinemia occurs frequently in patients who take atazanavir, including pregnant individuals. Refer to the atazanavir prescribing information for use of atazanavir in pregnancy.

Fetal/Neonatal Adverse Reactions

Atazanavir

Infants exposed to atazanavir in utero may develop severe hyperbilirubinemia during the first few days of life.

Data

Human Data

Atazanavir

The APR has received prospective reports of live births following exposure to atazanavir-containing regimens during pregnancy, including 1361 exposures in the first trimester and 737 exposures in second/third trimester. Birth defects occurred in live births in 30 of 1361 (2.2%, 95% CI: 1.5% to 3.1%) with first trimester exposure to atazanavir-containing regimens and 17 of 737 (2.3%, 95% CI: 1.3% to 3.7%) with second/third trimester exposure to atazanavir-containing regimens. There was no increase in the overall rate of birth defects for atazanavir compared with the background birth defect rate of 2.7% in the U.S. reference population of the MACDP.

Cobicistat

The APR has received prospective reports of live births following exposure to cobicistat-containing regimens during pregnancy, including 347 exposures in the first trimester and 79 exposures in the second/third trimester. Birth defects occurred in 13 of 347 (3.7%, 95% CI: 2.0% to 6.3%) live births with first trimester exposure and 1 of 79 (1.3%, 95% CI: 0.0% to 6.9%) with second/third trimester exposure to cobicistat-containing regimens. Among pregnant individuals in the U.S. reference population, the background rate of birth defects is 2.7%. There was no increase in the overall rate of birth defects for cobicistat compared with the background birth defect rate of 2.7% in the U.S. reference population of the MACDP. Methodological limitations of the APR include the use of MACDP as the external comparator group. Limitations of using an external comparator include differences in methodology and populations, as well as confounding due to the underlying disease.

Animal Data

Atazanavir

Atazanavir was administered orally to pregnant rats (at 0, 200, 600, and 1920 mg/kg/day) and rabbits (at 0, 4, 15, and 60 mg/kg/day) during organogenesis (on gestation Days 6 through 15 and 7 through 19, respectively). No significant toxicological effects were observed in embryo-fetal toxicity studies performed with atazanavir at exposures (AUC) approximately 1.2 times higher (rats) and 0.7 times (rabbits) human exposures at the MRHD. In a rat pre- and postnatal developmental study, atazanavir was administered orally at doses of 0, 50, 220, and 1000 mg/kg/day from gestation Day 6 to postnatal Day 20. At a maternal toxic dose (1000 mg/kg/day), atazanavir caused body weight loss or weight gain suppression in the animal offspring at atazanavir exposures (AUC) of approximately 1.3 times higher than human exposures at the MRHD.

Cobicistat

Cobicistat was administered orally to pregnant rats at doses of 0, 25, 50, 125 mg/kg/day on gestation Day 6 to 17. Maternal toxicity was noted at 125 mg/kg/day and was associated with increases in post-implantation loss and decreased fetal weights. No malformations were noted at doses up to 125 mg/kg/day. Systemic exposures (AUC) at 50 mg/kg/day in pregnant females were 1.4 times higher than the human exposures at the MRHD. In pregnant rabbits, cobicistat was administered orally at doses of 0, 20, 50, and 100 mg/kg/day during the gestation Days 7 to 20. No maternal or embryo/fetal effects were noted at the highest dose of 100 mg/kg/day. Systemic exposures (AUC) at 100 mg/kg/day were 3.3 times higher than exposures at the MRHD.

In a pre- and postnatal developmental study in rats, cobicistat was administered orally at doses of 0, 10, 30, and 75 mg/kg from gestation Day 6 to postnatal Day 20, 21, or 22. At doses of 75 mg/kg/day of cobicistat, neither maternal nor developmental toxicity was noted. Systemic exposures (AUC) at this dose were 0.9 times lower than exposures at the MRHD.

8.2 Lactation

Risk Summary

There is no information regarding the effects of EVOTAZ on the breastfed infant or on milk production.

Atazanavir has been detected in human milk. No data are available regarding atazanavir effects on milk production. Atazanavir was present in the milk of lactating rats and was associated with neonatal growth retardation that reversed after weaning. Cobicistat is present in rat milk (see Data). There is no information regarding the presence of cobicistat in human milk, the effects on the breastfed infant, or the effects on milk production. Potential risks of breastfeeding include: (1) HIV-1 transmission (in infants without HIV-1), (2) developing viral resistance (in infants with HIV-1), and (3) adverse reactions in a breastfed infant similar to those seen in adults.

Data

Animal Data

Cobicistat: During the prenatal and postnatal development toxicology study at doses up to 75 mg/kg/day, mean cobicistat milk to plasma ratio of up to 1.9 was measured 2 hours after administration to rats on lactation Day 10.

8.3 Females and Males of Reproductive Potential

Contraception

Atazanavir and cobicistat, components of EVOTAZ, interact with certain oral contraceptives [see Contraindications (4) and Drug Interactions (7.3)]. Nonhormonal forms of contraceptive should be considered.

8.4 Pediatric Use

The safety and effectiveness of EVOTAZ for the treatment of HIV-1 in pediatric participants weighing at least 35 kg was established through a study with components of EVOTAZ. Use of EVOTAZ for this indication is supported by evidence from adequate and well-controlled studies in adults, and by pharmacokinetic, safety, and virologic data from an open-label trial of components of EVOTAZ (Study GS-US-216-0128) in pediatric participants with HIV-1 aged 12 years and older. The safety in these participants through 48 weeks was similar to that in antiretroviral treatment-naive adults [see Adverse Reactions (6.1), Clinical Pharmacology (12.3), and Clinical Studies (14.2)].

Safety and effectiveness of EVOTAZ in the pediatric population weighing less than 35 kg have not been established. Atazanavir, a component of EVOTAZ, is not recommended for use in pediatric patients below the age of 3 months due to the risk of kernicterus.

8.5 Geriatric Use

Clinical studies with the components of EVOTAZ did not include sufficient numbers of participants aged 65 and older to determine whether they respond differently from younger participants. In general, appropriate caution should be exercised in the administration and monitoring of EVOTAZ in elderly patients reflecting the greater frequency of decreased hepatic, renal, or cardiac function, and of concomitant disease or other drug therapy [see Clinical Pharmacology (12.3)].

8.6 Renal Impairment

EVOTAZ is not recommended for use in treatment-experienced patients with HIV-1 who have end-stage renal disease managed with hemodialysis [see Dosage and Administration (2.3), Warnings and Precautions (5.3), and Clinical Pharmacology (12.3)].

8.7 Hepatic Impairment

EVOTAZ is not recommended for use in patients with any degree of hepatic impairment [see Dosage and Administration (2.4), Warnings and Precautions (5.7), and Clinical Pharmacology (12.3)].

10 OVERDOSAGE

Treatment for overdosage with EVOTAZ should consist of general supportive measures, including monitoring of vital signs and ECG, and observations of the patient’s clinical status. There is no specific antidote for overdose with EVOTAZ. Since atazanavir is extensively metabolized by the liver and both atazanavir and cobicistat are highly bound plasma proteins, it is unlikely that EVOTAZ will be significantly removed by hemodialysis or peritoneal dialysis.

Atazanavir: Human experience of acute overdose with atazanavir is limited. A single self-administered overdose of 29.2 g of atazanavir in a patient with HIV-1 (73 times the 400-mg recommended dose of atazanavir administered without a CYP3A inhibitor) was associated with asymptomatic bifascicular block and PR interval prolongation. These events resolved spontaneously. At atazanavir doses resulting in high atazanavir exposures, jaundice due to indirect (unconjugated) hyperbilirubinemia (without associated liver function test changes) or PR interval prolongation may be observed [see Warnings and Precautions (5.1, 5.10) and Clinical Pharmacology (12.2)].

11 DESCRIPTION

EVOTAZ® is a fixed-dose tablet for oral administration containing the active ingredients atazanavir and cobicistat. Atazanavir is an HIV-1 protease inhibitor. Cobicistat is a mechanism-based inhibitor of cytochrome P450 (CYP) enzymes of the CYP3A family. EVOTAZ tablets contain 342 mg of atazanavir sulfate, equivalent to 300 mg of atazanavir, and 150 mg of cobicistat, as well as the following inactive ingredients in the tablet core: croscarmellose sodium, crospovidone, hydroxypropyl cellulose, magnesium stearate, microcrystalline cellulose, silicon dioxide, sodium starch glycolate, and stearic acid. The tablets are film-coated with a coating material containing the following inactive ingredients: hypromellose, red iron oxide, talc, titanium dioxide, triacetin.

Atazanavir: Atazanavir is present as the sulfate salt. The chemical name for atazanavir sulfate is (3S,8S,9S,12S)-3,12-bis(1,1-dimethylethyl)-8-hydroxy-4,11-dioxo-9-(phenylmethyl)-6-[[4-(2-pyridinyl)phenyl]methyl]-2,5,6,10,13-pentaazatetradecanedioic acid dimethyl ester, sulfate (1:1). Its molecular formula is C38H52N6O7•H2SO4, which corresponds to a molecular weight of 802.9 (sulfuric acid salt). The free base molecular weight is 704.9. Atazanavir sulfate has the following structural formula:

Atazanavir sulfate is a white to pale-yellow crystalline powder. It is slightly soluble in water (4-5 mg/mL, free base equivalent) with the pH of a saturated solution in water being about 1.9 at 24 ± 3°C.

Cobicistat: The chemical name for cobicistat is 1,3-thiazol-5-ylmethyl [(2R,5R)-5-{[(2S)-2-[(methyl{[2-(propan-2-yl)-1,3-thiazol-4-yl]methyl}carbamoyl)amino]-4-(morpholin-4-yl)butanoyl]amino}-1,6-diphenylhexan-2-yl]carbamate. It has a molecular formula of C40H53N7O5S2 and a molecular weight of 776.0. It has the following structural formula:

Cobicistat is adsorbed onto silicon dioxide. Cobicistat on silicon dioxide is a white to pale yellow solid with a solubility of 0.1 mg/mL in water at 20°C.

12 CLINICAL PHARMACOLOGY

12.1 Mechanism of Action

EVOTAZ is a fixed-dose tablet consisting of the HIV-1 antiretroviral drug, atazanavir and the CYP3A inhibitor, cobicistat [see Clinical Pharmacology (12.4)].

12.2 Pharmacodynamics

Cardiac Electrophysiology

Atazanavir: In a thorough QT/QTc study in 72 healthy participants (Study AI424-076), atazanavir 400 mg and 800 mg (Cmax was 1.2 times and 2.4 times the Cmax observed with the recommended dosage of EVOTAZ, respectively) without a CYP3A inhibitor did not prolong the QTc interval to any clinically relevant extent. Asymptomatic prolongation of the PR interval was noted in participants receiving atazanavir. The mean (±SD) maximum change in PR interval from the predose for atazanavir 400 mg (n=65), atazanavir 800 mg (n=66), and placebo (n=67) was 24 (±15) msec, 60 (±25) msec, and 13 (±11) msec, respectively. Steady state atazanavir exposures (Cmax and AUCtau) observed in this healthy participant study exceeded those observed in participants treated with atazanavir coadministered with cobicistat. There is limited information on the potential for a pharmacodynamic interaction in humans between atazanavir and other drugs that prolong the PR interval of the electrocardiogram [see Warnings and Precautions (5.1)].

In 1793 participants with HIV-1 receiving antiretroviral regimens, QTc prolongation was comparable in the atazanavir-containing and comparator regimens. No atazanavir-treated healthy participant or participant with HIV-1 in clinical trials had a QTc interval >500 msec [see Warnings and Precautions (5.1)].

Cobicistat: In a thorough QT/QTc study conducted in 48 healthy participants (Study GS-US-216-0107), cobicistat 250 mg (1.7 times the recommended dosage in EVOTAZ) and 400 mg (2.7 times the recommended dosage in EVOTAZ) did not prolong the QTc interval to any clinically relevant extent. Asymptomatic prolongation of the PR interval was noted in participants receiving cobicistat. The maximum mean (95% upper confidence bound) difference in PR from placebo after baseline correction was 9.5 (12.1) msec for 250 mg and 20.2 (22.8) msec for 400 mg dose of cobicistat.

Effects on Serum Creatinine

The effect of cobicistat on serum creatinine was investigated in Study GS-US-216-0121, conducted in participants with normal renal function (eGFR ≥80 mL/min, N=12) and mild-to-moderate renal impairment (eGFR 50-79 mL/min, N=18). A statistically significant change in estimated glomerular filtration rate, calculated by Cockcroft-Gault method (eGFRCG) from baseline, was observed after 7 days of treatment with cobicistat 150 mg among participants with normal renal function (−9.9 ± 13.1 mL/min) and mild-to-moderate renal impairment (−11.9 ± 7.0 mL/min). No statistically significant changes in eGFRCG were observed compared to baseline for participants with normal renal function or mild-to-moderate renal impairment 7 days after cobicistat was discontinued. The actual glomerular filtration rate, as determined by the clearance of probe drug iohexol, was not altered from baseline following treatment with cobicistat among participants with normal renal function and mild-to-moderate renal impairment, indicating that cobicistat inhibits tubular secretion of creatinine, reflected as a reduction in eGFRCG, without affecting the actual glomerular filtration rate [see Warnings and Precautions (5.3)].

12.3 Pharmacokinetics

Absorption, Distribution, Metabolism, and Excretion

The pharmacokinetic (PK) properties of the components of EVOTAZ (atazanavir 300 mg and cobicistat 150 mg) were evaluated in healthy adult participants (Study AI424-511). Results are summarized in Table 6.

Table 6: Pharmacokinetic Properties of the Components of EVOTAZ
 | Atazanavir | Cobicistat
Absorption
Tmax (h) | 2.0 | 2.0
Effect of light meal (relative to fasting) AUC ratiob | 1.28 (1.17,1.40) | 1.24 (1.15,1.34)
Effect of high fat meal (relative to fasting) AUC ratiob | 0.96 (0.81,1.13) | 1.12 (1.01,1.23)
Effect of light meal (relative to fasting) C24 ratiob | 1.35 (1.22,1.50) | ND
Effect of high fat meal (relative to fasting) C24 ratiob | 1.23 (1.02,1.48) | ND
Distribution
% Bound to human plasma proteins | 86 | ~98
Source of protein binding data | In vitro | In vitro
Blood-to-plasma ratio | ND | 0.5
Metabolism
Metabolism | CYP3A (major) Glucuronidation, N-dealkylation, hydrolysis, oxygenation with dehydrogenation (minor) | CYP3A (major) CYP2D6 (minor)
Elimination
Major route of elimination | Metabolism | Metabolism
t1/2 (h) | 7.2a | 3.5
% Of dose excreted in urine | ND | 8.2c
% Of dose excreted in feces | ND | 86.2c
a Following EVOTAZ dosing under fasted conditions.
b Values refer to geometric mean ratio (fed / fasted) and (90% confidence interval).
c Dosing in mass balance study: cobicistat (single dose administration of [14C] cobicistat after multiple dosing of cobicistat for six days).
ND = not determined.

The pharmacokinetics of atazanavir was evaluated in participants with HIV-1 who received atazanavir 300 mg coadministered with cobicistat 150 mg in combination with emtricitabine/tenofovir DF. The steady-state pharmacokinetic parameters of atazanavir coadministered with cobicistat are shown in Table 7 [see Clinical Studies (14)].

Table 7: Pharmacokinetic Parameters (Mean ± SD) of Atazanavir in the Pharmacokinetic Substudy of Study GS-US-216-0114
Parameter | Atazanavir coadministered with cobicistat and emtricitabine/tenofovir DF (n=22)
AUC (µg•h/mL) | 46.13 ± 26.18
Cmax (µg/mL) | 3.91 ± 1.94
Ctau (µg/mL) | 0.80 ± 0.72

Specific Populations

Pediatric

In pediatric participants aged 12 to less than 18 years who received atazanavir 300 mg coadministered with cobicistat 150 mg (N=12), atazanavir exposures (AUCtau, Cmax, and Ctau) were 20-60% higher than in adults; the increases were not considered clinically significant (Table 8).

Table 8: Multiple Dose Pharmacokinetic Parameters of Atazanavir Following Coadministration of Atazanavir with Cobicistat in Pediatric Participants with HIV-1 Weighing at Least 35 kg
Atazanavir PK Parameter | Geometric Mean (CV%)
Atazanavir PK Parameter | Pediatric participants (N=12)a | Adult participants (N=30)b
AUCtau (µg/hr/mL) | 49.48 (49.1) | 39.96 (52.1)
Cmax (µg/mL) | 4.32 (49.9) | 3.54 (45.8)
Ctau (µg/mL) | 0.91 (96.4) | 0.58 (84.7)
CV=Coefficient of Variation
a From intensive PK analysis of Study GS-US-216-0128
b From pooled intensive PK analysis of trials with atazanavir + cobicistat.

Renal Impairment

Atazanavir: In healthy participants, the renal elimination of unchanged atazanavir was approximately 7% of the administered dose. In study AI424-105, atazanavir was studied in adult participants (n=20) with severe renal impairment (estimated creatinine clearance <30 mL/min, using 24-hour urinary creatinine and serum creatinine levels), including those on hemodialysis, at multiple doses of 400 mg once daily. The mean atazanavir Cmax was 9% lower, AUC was 19% higher, and Cmin was 96% higher in participants with severe renal impairment not undergoing hemodialysis (n=10), than in age-, weight-, and gender-matched participants with normal renal function. In a 4-hour dialysis session, 2.1% of the administered dose was removed. When atazanavir was administered either prior to, or following hemodialysis (n=10), the geometric means for Cmax, AUC, and Cmin were approximately 25% to 43% lower compared to participants with normal renal function. The mechanism of this decrease is unknown.

Cobicistat: No clinically relevant differences in cobicistat pharmacokinetics were observed between participants with severe renal impairment (estimated creatinine clearance <30 mL/min, using the Cockcroft-Gault method) and healthy participants in Study GS-US-216-0124 [see Use in Specific Populations (8.6)].

Hepatic Impairment

EVOTAZ has not been studied in patients with hepatic impairment.

Atazanavir: Increased concentrations of atazanavir are expected in those with moderately or severely impaired hepatic function (Study AI424-015).

Cobicistat: No clinically relevant differences in cobicistat pharmacokinetics were observed between participants with moderate hepatic impairment (Child-Pugh Class B) and healthy participants (Study GS-US-183-0133). The effect of severe hepatic impairment (Child-Pugh Class C) on the pharmacokinetics of cobicistat has not been studied [see Use in Specific Populations (8.7)].

Pregnancy and Postpartum

Pharmacokinetic data from studies conducted in pregnant individuals receiving cobicistat showed substantially lower exposures during the second and third trimesters, and consequently also for the coadministered antiretroviral agent. Consult the full prescribing information for cobicistat for additional information. Pharmacokinetic data from the evaluation of atazanavir and cobicistat in a limited number of pregnant individuals showed a similar trend in lower exposures of the antiretroviral component, atazanavir.

Gender, Age, and Race

Atazanavir: No clinically important differences in atazanavir pharmacokinetics were observed based on age or gender.

Cobicistat: No clinically relevant differences in cobicistat pharmacokinetics were observed based on race or gender.

Assessment of Drug Interactions

Atazanavir has been shown in vivo not to induce its own metabolism, nor to increase the biotransformation of some drugs metabolized by CYP3A. In a multiple-dose study, atazanavir decreased the urinary ratio of endogenous 6β-OH cortisol to cortisol versus baseline, indicating that CYP3A production was not induced.

The effects of cobicistat on the exposure of coadministered drugs are summarized in Table 9.

Table 9: Drug Interactions: Pharmacokinetic Parameters for Coadministered Drugs in the Presence of Cobicistata,b
Note: The information listed below is not a comprehensive list of all the available drug interaction data for concomitant medications with cobicistat-containing regimens. Please refer to the U.S. prescribing information for antiretroviral medications administered in combination with cobicistat for additional drug interaction information.
Coadministered Drug | Coadministered Drug Dose/Schedule | Cobicistat Dose/Schedule | Ratio (90% Confidence Interval) of Coadministered Drug Pharmacokinetic Parameters with/without cobicistat; No effect = 1.00
Coadministered Drug | Coadministered Drug Dose/Schedule | Cobicistat Dose/Schedule | Cmax | AUC
atorvastatin | 10 mg single dose (n=16) | 150 mg QD (n=16) | 18.85b (13.53, 26.27) | 9.22b (7.58, 11.22)
desipramine | 50 mg single dose (n=8) | 150 mg QD (n=8) | 1.24 (1.08, 1.44) | 1.65 (1.36, 2.02)
digoxin | 0.5 mg single dose (n=22) | 150 mg QD (n=22) | 1.41 (1.29, 1.55) | 1.08 (1.00, 1.17)
drospirenone/ ethinyl estradiol | 3 mg drospirenone single dose (n=14) | 150 mg QD (n=14) | 1.12b (1.05, 1.19) | 2.30b (2.00, 2.64)
drospirenone/ ethinyl estradiol | 0.02 ethinyl estradiol single dose (n=14) | 150 mg QD (n=14) | 0.82b (0.76, 0.89) | 0.78b (0.73, 0.85)
efavirenz | 600 mg single dose (n=17) | 150 mg QD (n=17) | 0.87 (0.80, 0.94) | 0.93 (0.89, 0.97)
rosuvastatin | 10 mg single dose (n=16) | 150 mg QD (n=16) | 10.58b (8.72, 12.83) | 3.42b (2.87, 4.07)
a All interaction studies conducted in healthy participants.
b Studies of cobicistat conducted in the presence of atazanavir 300 mg.

12.4 Microbiology

Mechanism of Action

EVOTAZ is a fixed-dose tablet of atazanavir and the CYP3A inhibitor cobicistat. Atazanavir is an azapeptide HIV-1 protease inhibitor that selectively inhibits the virus-specific processing of viral Gag and Gag-Pol polyproteins in HIV-1-infected cells, thus preventing formation of mature virions. Cobicistat is a mechanism-based inhibitor of cytochrome P450 3A (CYP3A). Inhibition of CYP3A-mediated metabolism by cobicistat increases the systemic exposure of the CYP3A substrate atazanavir.

Antiviral Activity in Cell Culture

Atazanavir exhibits anti−HIV-1 activity with a mean 50% effective concentration (EC50 value) in the absence of human serum of 2 to 5 nM against a variety of laboratory and clinical HIV-1 isolates grown in peripheral blood mononuclear cells, macrophages, CEM-SS cells, and MT‑2 cells. Atazanavir has activity against HIV-1 Group M subtype viruses A, B, C, D, AE, AG, F, G, and J isolates in cell culture. Atazanavir has variable activity against HIV-2 isolates (1.9-32 nM), with EC50 values above the EC50 values of failure isolates. Two-drug combination antiviral activity studies with atazanavir showed no antagonism in cell culture with NNRTIs (delavirdine, efavirenz, and nevirapine), protease inhibitors (amprenavir, indinavir, lopinavir, nelfinavir, ritonavir, and saquinavir), NRTIs (abacavir, didanosine, emtricitabine, lamivudine, stavudine, tenofovir, zalcitabine, and zidovudine), the HIV-1 fusion inhibitor enfuvirtide, and two compounds used in the treatment of viral hepatitis, adefovir and ribavirin, without enhanced cytotoxicity.

Cobicistat does not inhibit recombinant HIV-1 protease in a biochemical assay and has no detectable antiviral activity in cell culture against HIV-1, hepatitis B or C virus. The antiviral activity in cell culture of selected HIV-1 antiretroviral drugs was not antagonized by cobicistat.

Resistance

In Cell Culture: HIV-1 isolates with a decreased susceptibility to atazanavir have been selected in cell culture and obtained from patients treated with atazanavir coadministered with ritonavir. HIV-1 isolates with 93- to 183-fold reduced susceptibility to atazanavir from three different viral strains were selected in cell culture by 5 months. The substitutions in these HIV-1 viruses that contributed to atazanavir resistance include I50L, N88S, I84V, A71V, and M46I. Changes were also observed at the protease cleavage sites following drug selection. Recombinant viruses containing the I50L substitution without other major protease inhibitor substitutions were growth impaired and displayed increased susceptibility in cell culture to other protease inhibitors (amprenavir, indinavir, lopinavir, nelfinavir, ritonavir, and saquinavir). The I50L and I50V substitutions yielded selective resistance to atazanavir and amprenavir, respectively, and did not appear to be cross-resistant.

Clinical Studies: Resistance to EVOTAZ is driven by atazanavir as cobicistat lacks antiviral activity. For the complete atazanavir resistance-associated substitutions, refer to the atazanavir full prescribing information.

Clinical Studies of Treatment-Naive Adult Participants Receiving Atazanavir 300 mg Coadministered with Cobicistat 150 mg: In an analysis of adult participants who received atazanavir coadministered with cobicistat through Week 144 (Study GS-US-216-0114), evaluable genotypic data from paired baseline and treatment-failure isolates from participants who had HIV-1 RNA greater than or equal to 400 copies/mL were available for all 21 virologic failures in this group (6%, 21/344). Among the 21 participants, 3 developed the emtricitabine resistance-associated substitution M184V. No participant developed the tenofovir resistance-associated substitution K65R or K70E, or any primary resistance substitution associated with protease inhibitors. In the ritonavir group, evaluable genotypic data were available for all 19 virologic failures (5%, 19/348). Among the 19 participants, 1 developed the emtricitabine resistance-associated substitution M184V with no tenofovir or protease inhibitor resistance-associated substitutions.

Clinical Study of Pediatric Participants Receiving Atazanavir Coadministered with Cobicistat: In an as-treated analysis of pediatric participants between the ages of 12 to less than 18 years who received atazanavir coadministered with cobicistat plus two NRTIs in Study GS-US-216-0128, 3 of 14 participants qualified for resistance analysis through Week 48; 1 had evaluable data and no significant resistance-associated substitutions in protease or reverse transcriptase [see Clinical Studies (14.2)].

Cross-Resistance

Cross-resistance among protease inhibitors has been observed. Baseline phenotypic and genotypic analyses of clinical isolates from atazanavir clinical trials of protease inhibitor-experienced participants with HIV-1 showed that isolates cross-resistant to multiple protease inhibitors were cross-resistant to atazanavir. Greater than 90% of the isolates with substitutions that included I84V or G48V were resistant to atazanavir. Greater than 60% of isolates containing L90M, G73S/T/C, A71V/T, I54V, M46I/L, or a change at V82 were resistant to atazanavir, and 38% of isolates containing a D30N substitution in addition to other changes were resistant to atazanavir. Isolates resistant to atazanavir were also cross-resistant to other protease inhibitors with >90% of the isolates resistant to indinavir, lopinavir, nelfinavir, ritonavir, and saquinavir, and 80% resistant to amprenavir. In treatment-experienced patients, protease inhibitor-resistant viral isolates that developed the I50L substitution in addition to other protease inhibitor resistance-associated substitution were also cross-resistant to other protease inhibitors.

International AIDS Society (IAS)-defined protease inhibitor resistance substitutions, depending on the number and type, may confer a reduced virologic response to atazanavir. Please refer to the “Baseline Genotype/Phenotype and Virologic Outcome Analyses” section in the atazanavir full prescribing information.

13 NONCLINICAL TOXICOLOGY

13.1 Carcinogenesis, Mutagenesis, Impairment of Fertility

Carcinogenesis

Atazanavir: Long-term carcinogenicity studies in mice and rats were carried out with atazanavir for two years. In the mouse study, drug-related increases in hepatocellular adenomas were found in females at 360 mg/kg/day. The systemic drug exposure (AUC) at the NOAEL in females, (120 mg/kg/day) was 2.8 times and in males (80 mg/kg/day) was 2.9 times higher than those in humans at the clinical dose (300 mg/day atazanavir coadministered with 100 mg/day ritonavir, nonpregnant patients). In the rat study, no drug-related increases in tumor incidence were observed at doses up to 1200 mg/kg/day, for which AUCs were 1.1 (males) or 3.9 (females) times those measured in humans at the clinical dose.

Cobicistat: In a long-term carcinogenicity study in mice, no drug-related increases in tumor incidence were observed at doses up to 50 and 100 mg/kg/day (males and females, respectively). Cobicistat exposures at these doses were approximately 7 (male) and 16 (females) times, respectively, the human systemic exposure at the therapeutic daily dose. In a long-term carcinogenicity study of cobicistat in rats, an increased incidence of follicular cell adenomas and/or carcinomas in the thyroid gland was observed at doses of 25 and 50 mg/kg/day in males, and at 30 mg/kg/day in females. The follicular cell findings are considered to be rat-specific, secondary to hepatic microsomal enzyme induction and thyroid hormone imbalance, and are not relevant for humans. At the highest doses tested in the rat carcinogenicity study, systemic exposures were approximately 2 times the human systemic exposure at the therapeutic daily dose.

Mutagenesis

Atazanavir: Atazanavir tested positive in an in vitro clastogenicity test using primary human lymphocytes, in the absence and presence of metabolic activation. Atazanavir tested negative in the in vitro Ames reverse-mutation assay, in vivo micronucleus and DNA repair tests in rats, and in vivo DNA damage test in rat duodenum (comet assay).

Cobicistat: Cobicistat was not genotoxic in the reverse mutation bacterial test (Ames test), mouse lymphoma or rat micronucleus assays.

Impairment of Fertility

Atazanavir: At the systemic drug exposure levels (AUC) 0.9 (in male rats) or 2.3 (in female rats) times that of the human clinical dose, (300 mg/day atazanavir coadministered with 100 mg/day ritonavir) significant effects on mating, fertility, or early embryonic development were not observed.

Cobicistat: Cobicistat did not affect fertility in male or female rats at daily exposures (AUC) approximately 3-fold higher than human exposures at the recommended 150 mg daily dose. Fertility was normal in the offspring of rats exposed daily from before birth (in utero) through sexual maturity at daily exposures (AUC) of approximately similar human exposures at the recommended 150 mg daily dose.

14 CLINICAL STUDIES

14.1 Clinical Trial Results in Treatment-Naive Adult Participants with HIV-1 Study GS-US-216-0114

The safety and efficacy of atazanavir coadministered with cobicistat were evaluated in a randomized, double-blind, active-controlled trial (Study GS-US-216-0114 [NCT01108510]) in treatment-naive participants with HIV-1 infection with baseline estimated creatinine clearance above 70 mL/min (N=692). Participants were randomized in a 1:1 ratio to receive either atazanavir 300 mg coadministered with cobicistat 150 mg once daily or atazanavir 300 mg coadministered with ritonavir 100 mg once daily. All participants received concomitant treatment with 300 mg of tenofovir DF and 200 mg of emtricitabine once a day administered as a single tablet. Randomization was stratified by screening HIV-1 RNA level (≤100,000 copies/mL or >100,000 copies/mL).

The mean age of participants was 37 years (range: 19-70); 83% were male, 60% were White, 18% were Black, and 12% were Asian. The mean baseline plasma HIV-1 RNA was 4.8 log10 copies/mL (range: 3.2-6.4). The mean baseline CD4+ cell count was 352 cells/mm^3 (range: 1-1455) and 17% had CD4+ cell counts ≤200 cells/mm^3. Forty percent (40%) of patients had baseline viral loads >100,000 copies/mL.

Virologic outcomes in Study GS-US-216-0114 through Week 144 are presented in Table 10. In Study GS-US-216-0114, the mean increase from baseline in CD4+ cell count at Week 144 was 281 cells/mm^3 in patients receiving atazanavir coadministered with cobicistat and 297 cells/mm^3 in patients receiving atazanavir coadministered with ritonavir.

Table 10: Virologic Outcomes of Randomized Treatment of Study GS-US-216-0114 in Treatment-Naive Adults with HIV-1 at Week 144a
 | Atazanavir 300 mg coadministered with cobicistat 150 mg (once daily) + emtricitabine/tenofovir disoproxil fumarate (n=344) | Atazanavir 300 mg coadministered with ritonavir 100 mg + emtricitabine/tenofovir disoproxil fumarate (n=348)
HIV-1 RNA <50 copies/mL | 72% | 74%
Treatment Difference | −2.1% (95% CI = −8.7%, 4.5%)
HIV-1 RNA ≥50 copies/mLb | 8% | 5%
No Virologic Data at Week 48 Window | 20% | 21%
Discontinued Study Drug Due to AE or Deathc | 11% | 11%
Discontinued Study Drug Due to Other Reasons and Last Available HIV-1 RNA <50 copies/mLd | 8% | 10%
Missing Data During Window, but on Study Drug | <1% | <1%
a Week 144 window is between Day 967 and 1050 (inclusive).
b Includes participants who had ≥50 copies/mL in the Week 48 window; participants who discontinued early due to lack or loss of efficacy; participants who discontinued for reasons other than an adverse event, death or lack or loss of efficacy and at the time of discontinuation had a viral value of ≥50 copies/mL.
c Includes participants who discontinued due to adverse event or death at any time point from Day 1 through the time window if this resulted in no virologic data on treatment during the specified window. There were no deaths reported in Study GS-US-216-0114.
d Includes participants who discontinued for reasons other than an adverse event, death, or lack or loss of efficacy (e.g., withdrew consent, lost to follow-up, etc).

14.2 Clinical Trial Results in Virologically Suppressed Pediatric Participants with HIV-1 Infection– Study GS-US-216-0128

Study GS-US-216-0128 (NCT02016924) was a Phase 2/3 multicenter, open-label trial to evaluate the pharmacokinetics, safety, and efficacy of atazanavir coadministered with cobicistat in pediatric participants ages 12 years and older with HIV-1 who were virologically suppressed and had a baseline estimated creatinine clearance ≥90 mL/min/1.73 m^2. Participants were on a stable antiretroviral regimen (for at least 3 months), consisting of atazanavir administered with ritonavir, combined with 2 nucleotide reverse transcriptase inhibitors (NRTIs). They were switched from ritonavir to cobicistat 150 mg once daily and continued atazanavir (N=14) and 2 NRTIs.

The mean age of participants was 14 years (range 12–17 years); median weight was 53 kg; 71% were male, 57% were Asian, 29% were White, 14% were Black, and 71% were not Hispanic or Latino. At baseline, 13/14 participants had plasma HIV-1 RNA <50 copies/mL and 1 participant had plasma HIV‑1 RNA of 50 copies/mL.

In participants who switched to atazanavir coadministered with cobicistat, 93% (13/14) of participants remained suppressed (HIV-1 RNA <50 copies/mL), and 1 participant experienced virologic failure at Week 48. From a median baseline CD4+ cell count and CD4+% of 770 cells/mm^3 (range 486 to 1765 cells/mm^3) and 33% (range 23% to 45%), respectively, the median change from baseline in CD4+ cell count and CD4+% at Week 48 was ‑60 cells/mm^3 (range ‑500 to 705 cells/mm^3) and ‑0.3% (range ‑6% to 8%), respectively.

16 HOW SUPPLIED/STORAGE AND HANDLING

EVOTAZ® tablets, 300 mg atazanavir and 150 mg cobicistat, are oval, biconvex, pink, film-coated, debossed with “3641” on one side and plain on the other side. Each bottle contains 30 tablets (NDC-0003-3641-11), a silica gel desiccant and is closed with a child-resistant closure.

Store EVOTAZ tablets at 25°C (77°F); excursions permitted between 15°C and 30°C (59°F and 86°F) [see USP Controlled Room Temperature]. Keep container tightly closed.

17 PATIENT COUNSELING INFORMATION

Advise the patient to read the FDA-approved patient labeling (Patient Information).

Instructions for Use

Advise patients to take EVOTAZ with food every day and that EVOTAZ must always be used in combination with other antiretroviral drugs. Inform patients to avoid missing doses as it can result in development of resistance, and not to discontinue therapy without consulting with their healthcare provider. Advise patients if a dose of EVOTAZ is missed, they should take the dose as soon as possible and then return to their normal schedule; however, if a dose is skipped, the patient should not double the next dose [see Dosage and Administration (2.2, 2.3)].

Drug Interactions

EVOTAZ may interact with many drugs; therefore, inform patients of the potential for serious drug interactions with EVOTAZ, and that some drugs are contraindicated with EVOTAZ and other drugs require dosage adjustment. Advise patients to report to their healthcare provider the use of any other prescription, nonprescription medication, or herbal products, particularly St. John’s wort.

Instruct patients receiving hormonal contraceptives to use additional or alternative non-hormonal contraceptive measures during therapy with EVOTAZ because no data are available to make recommendations regarding use of hormonal contraceptives and atazanavir coadministered with cobicistat [see Contraindications (4), Warnings and Precautions (5.8, 5.9), and Drug Interactions (7)].

Cardiac Conduction Abnormalities

Inform patients that EVOTAZ may produce changes in the electrocardiogram (e.g., PR prolongation). Advise patients to consult their healthcare provider if they are experiencing symptoms such as dizziness or lightheadedness [see Warnings and Precautions (5.1)].

Severe Skin Reactions

Inform patients that mild rashes without other symptoms have been reported with atazanavir use. These rashes go away within two weeks with no change in treatment. However, inform patients there have been reports of severe skin reactions (e.g., Stevens-Johnson syndrome, erythema multiforme, and toxic skin eruptions) with atazanavir use. Advise patients to seek medical evaluation immediately if signs or symptoms of severe skin reactions or hypersensitivity reactions develop (including, but not limited to, severe rash or rash accompanied by fever, general malaise, muscle or joint aches, blisters, oral lesions, conjunctivitis, or facial edema) [see Warnings and Precautions (5.2)].

Chronic Kidney Disease

Inform patients that treatment with EVOTAZ may lead to the development of chronic kidney disease, and to maintain adequate hydration while taking EVOTAZ [see Warnings and Precautions (5.5)].

Nephrolithiasis and Cholelithiasis

Inform patients that kidney stones and/or gallstones have been reported with atazanavir use. Some patients with kidney stones and/or gallstones required hospitalization for additional management and some had complications [see Warnings and Precautions (5.6)].

Hyperbilirubinemia

Inform patients that asymptomatic elevations in indirect bilirubin have occurred in patients receiving atazanavir, a component of EVOTAZ. Tell patients this may be accompanied by yellowing of the skin or whites of the eyes and alternative antiretroviral therapy may be considered if they have cosmetic concerns [see Warnings and Precautions (5.10)].

Immune Reconstitution Syndrome

Advise patients to inform their healthcare provider immediately of any symptoms of infection, as in some patients with advanced HIV-1 (AIDS), signs and symptoms of inflammation from previous infections may occur soon after anti-HIV-1 treatment is started [see Warnings and Precautions (5.11)].

Fat Redistribution

Inform patients that redistribution or accumulation of body fat may occur in patients receiving antiretroviral therapy including protease inhibitors and that the cause and long-term health effects of these conditions are not known at this time [see Warnings and Precautions (5.13)].

Not Recommended During Pregnancy

Advise patients that EVOTAZ is not recommended during pregnancy and to alert their healthcare provider if they get pregnant while taking EVOTAZ [see Use in Specific Populations (8.1)].

Pregnancy Registry

Inform patients that there is a pregnancy exposure registry to monitor fetal outcomes of pregnant individuals exposed to EVOTAZ during pregnancy [see Use in Specific Populations (8.1)].

Lactation

Instruct patients with HIV-1 that the potential risks of breastfeeding include: (1) HIV-1 transmission to infants without HIV-1, (2) developing viral resistance in infants with HIV-1, and (3) adverse reactions in a breastfed infant similar to those seen in adults [see Use in Specific Populations (8.2)].

Manufactured for:

Bristol-Myers Squibb Company

Princeton, NJ 08543 USA

EVOTAZ is a trademark of Bristol-Myers Squibb Company.

PATIENT INFORMATION

EVOTAZ® (EV-oh-taz)
(atazanavir and cobicistat) tablet

What is EVOTAZ?

EVOTAZ is a prescription medicine that is used with other human immunodeficiency virus-1 (HIV-1) medicines to treat HIV-1 infection in adults and in children weighing at least 77 pounds (35 kg).

HIV-1 is the virus that causes Acquired Immunodeficiency Syndrome (AIDS).

EVOTAZ contains the prescription medicines atazanavir and cobicistat.

It is not known if EVOTAZ is safe and effective in children weighing less than 77 pounds (35 kg).

Do not take EVOTAZ if you:

- are allergic to any of the ingredients in EVOTAZ. See the end of this leaflet for a complete list of ingredients in EVOTAZ.
- are taking any of the following medicines. Taking EVOTAZ with these medicines may affect how EVOTAZ works. EVOTAZ may cause serious life-threatening side effects, or death when used with these medicines:

- alfuzosin
- apalutamide
- carbamazepine
- colchicine, if you have liver or kidney problems
- dronedarone
- drospirenone and ethinyl estradiol
- elbasvir and grazoprevir
- encorafenib
- ergot-containing medicines, including:
- dihydroergotamine
- ergotamine
- methylergonovine
- glecaprevir and pibrentasvir
- indinavir
- irinotecan
- ivosidenib

- lovastatin
- lomitapide
- lurasidone
- midazolam, when taken by mouth for sedation
- nevirapine
- phenobarbital
- phenytoin
- pimozide
- ranolazine
- rifampin
- sildenafil, when used for the treatment of pulmonary arterial hypertension (PAH)
- simvastatin
- St. John’s wort (Hypericum perforatum), or a product that contains St. John’s wort
- triazolam

Before taking EVOTAZ, tell your healthcare provider about all of your medical conditions, including if you:

- have heart problems
- have liver problems, including hepatitis B or C virus
- have kidney problems
- are receiving dialysis treatment
- have diabetes
- have hemophilia
- are pregnant or plan to become pregnant. It is not known if EVOTAZ will harm your unborn baby.
  - EVOTAZ should not be taken during pregnancy, because the EVOTAZ levels in your blood may be lower during pregnancy and may not control your HIV-1.
  - Tell your healthcare provider right away if you become pregnant during treatment with EVOTAZ.
  - Your healthcare provider may prescribe different medicines if you become pregnant during treatment with EVOTAZ.
  - People who are pregnant have developed a serious condition called lactic acidosis (a build-up of lactic acid in the blood) when taking EVOTAZ with other HIV-1 medicines called nucleoside analogues.
  - Hormonal forms of birth control, such as injections, vaginal rings or implants, contraceptive patches, and some birth control pills may not work during treatment with EVOTAZ. Talk to your healthcare provider about forms of birth control that may be used during treatment with EVOTAZ.
  - Pregnancy Exposure Registry. There is a pregnancy exposure registry for people who take EVOTAZ during pregnancy. The purpose of this registry is to collect information about the health of you and your baby. Talk to your healthcare provider about how you can take part in this registry.
- are breastfeeding or plan to breastfeed. EVOTAZ can pass into your breast milk.
  - Talk to your healthcare provider about the following risks to your baby from breastfeeding during treatment with EVOTAZ:
- The HIV-1 virus may pass to your baby if your baby does not have HIV-1.
- The HIV-1 virus may become harder to treat if your baby has HIV-1.
- Your baby may get side effects from EVOTAZ.

Tell your healthcare provider about all the medicines you take, including prescription and over-the-counter medicines, vitamins, and herbal supplements.

Some medicines interact with EVOTAZ. Keep a list of your medicines to show your healthcare provider and pharmacist.

- You can ask your healthcare provider or pharmacist for a list of medicines that interact with EVOTAZ.
- Do not start taking a new medicine without telling your healthcare provider. Your healthcare provider can tell you if it is safe to take EVOTAZ with other medicines.

How should I take EVOTAZ?

- Take EVOTAZ exactly as your healthcare provider tells you.
- Do not change your dose or stop taking EVOTAZ without talking to your healthcare provider.
- Stay under a healthcare provider’s care during treatment with EVOTAZ.
- EVOTAZ must be used with other HIV-1 medicines.
- Take EVOTAZ 1 time a day with food.
- Do not miss a dose of EVOTAZ. If you miss a dose of EVOTAZ, take it as soon as possible. Take your next dose at your normal scheduled time. Do not take 2 doses at the same time to make up for a missed dose.
- When your EVOTAZ supply starts to run low, get more from your healthcare provider or pharmacy. This is very important because the amount of virus in your blood may increase if the medicine is stopped for even a short time. The virus may develop resistance to EVOTAZ and become harder to treat.
- If you take too much EVOTAZ, call your healthcare provider or go to the nearest hospital emergency room right away.

What are the possible side effects of EVOTAZ?

EVOTAZ can cause serious side effects, including:

- A change in the way your heart beats (heart rhythm change). If you have certain heart rhythm problems, your healthcare provider may check your heart rhythm with a test called an electrocardiogram (ECG). Tell your healthcare provider right away if you get dizzy or lightheaded. These could be symptoms of a heart problem.
- Severe skin reactions. Skin rash is common with EVOTAZ but can sometimes be severe. Skin rash usually goes away within 2 weeks without any change in treatment. Severe rash may develop with other symptoms which could be serious. Call your healthcare provider or go to the nearest hospital emergency room right away if you develop a severe rash or a rash with any of the following symptoms:

- general feeling of discomfort or “flu-like” symptoms
- fever
- muscle or joint aches
- swelling of your face

- red or inflamed eyes, like “pink eye” (conjunctivitis)
- blisters
- mouth sores
- painful, warm, or red lump under your skin

- Kidney problems. EVOTAZ, when taken with certain other medicines, can cause new or worsening kidney problems, including kidney failure. Your healthcare provider should check your kidneys before you start EVOTAZ and during treatment.
- Chronic kidney disease. EVOTAZ may affect how well your kidneys work. Your healthcare provider will do blood and urine tests to check your kidneys before you start EVOTAZ and during treatment. Drink plenty of fluids during treatment with EVOTAZ.
- Kidney stones have happened in some people who take atazanavir, one of the medicines in EVOTAZ, and sometimes may lead to hospitalization. Tell your healthcare provider right away if you get symptoms of kidney stones, which may include pain in your low back or low stomach area, blood in your urine, or pain when you urinate.
- Gallbladder stones have happened in some people who take atazanavir, one of the medicines in EVOTAZ, and sometimes may lead to hospitalization. Tell your healthcare provider right away if you get symptoms of gallbladder problems, which may include:

- pain in the right or middle upper stomach area
- fever

- nausea and vomiting
- your skin or the white part of your eyes turns yellow

- Liver problems. If you have liver problems, including hepatitis B or C virus, your liver problems may get worse when you take EVOTAZ. Your healthcare provider will do blood tests to check your liver before you start EVOTAZ and during treatment. Tell your healthcare provider right away if you get any of the following symptoms:

- your skin or the white part of your eyes turns yellow
- dark (tea-colored) urine
- light colored stools

- nausea
- itching
- stomach-area pain

- Yellowing of the skin or the white part of your eyes is common with EVOTAZ but may be a symptom of a serious problem. These effects may be due to increases in bilirubin levels in the blood (bilirubin is made by the liver). Tell your healthcare provider right away if your skin or the white part of your eyes turns yellow.
- Changes in your immune system (Immune Reconstitution Syndrome) can happen when you start taking HIV-1 medicines. Your immune system may get stronger and begin to fight infections that have been hidden in your body for a long time. Tell your healthcare provider if you start having new symptoms after starting EVOTAZ.
- Diabetes and high blood sugar (hyperglycemia). New or worsening diabetes and hyperglycemia have happened in people who take protease inhibitor medicines like EVOTAZ. Some people have had to start taking medicine to treat diabetes or have had to change their diabetes medicine. Tell your healthcare provider if you notice an increase in thirst or if you start urinating more often during treatment with EVOTAZ.
- Changes in body fat can happen in people taking HIV-1 medicines. These changes may include increased amount of fat in the upper back and neck (“buffalo hump”), breast, and around the middle of your body (trunk). Loss of fat from the legs, arms, and face may also happen. The exact cause and long-term health effects of these conditions are not known.
- Increased bleeding problems in people with hemophilia have happened when taking protease inhibitors including EVOTAZ.

The most common side effects of EVOTAZ include yellowing of the skin and rash.

These are not all the possible side effects of EVOTAZ.

Call your doctor for medical advice about side effects. You may report side effects to FDA at 1-800-FDA-1088.

How should I store EVOTAZ?

- Store EVOTAZ tablets at room temperature between 68°F and 77°F (20°C and 25°C).
- The EVOTAZ bottle contains a desiccant that helps keep your medicine dry.
- The EVOTAZ bottle has a child-resistant closure.
- Keep tablets in a tightly closed container.

Keep EVOTAZ and all medicines out of the reach of children.

General information about the safe and effective use of EVOTAZ.

Medicines are sometimes prescribed for purposes other than those listed in a Patient Information leaflet. Do not use EVOTAZ for a condition for which it was not prescribed. Do not give EVOTAZ to other people, even if they have the same symptoms that you have. It may harm them.

You can ask your pharmacist or healthcare provider for information about EVOTAZ that is written for health professionals.

What are the ingredients in EVOTAZ?

Active ingredients: atazanavir and cobicistat

Inactive ingredients:

Tablet Core: croscarmellose sodium, crospovidone, hydroxypropyl cellulose, magnesium stearate, microcrystalline cellulose, silicon dioxide, sodium starch glycolate, and stearic acid.

Film coat: hypromellose, red iron oxide, talc, titanium dioxide, and triacetin.

Manufactured for:
Bristol-Myers Squibb Company

Princeton, NJ 08543 USA

EVOTAZ is a trademark of Bristol-Myers Squibb Company.

For more information, call 1‑800‑321‑1335.

This Patient Information has been approved by the U.S. Food and Drug Administration Revised: 05/2025

EVOTAZ (atazanavir and cobicistat) tablet Representative Packaging

See HOW SUPPLIED section for a complete list of available packages of EVOTAZ.

NDC 0003-3641-11
30 Tablets
EVOTAZ®
(atazanavir and cobicistat) tablets
300 mg/150 mg
Rx only
Take with food.
Note to pharmacist: Do not cover ALERT box with pharmacy label.
ALERT: Find out about medicines that should NOT be taken with EVOTAZ®